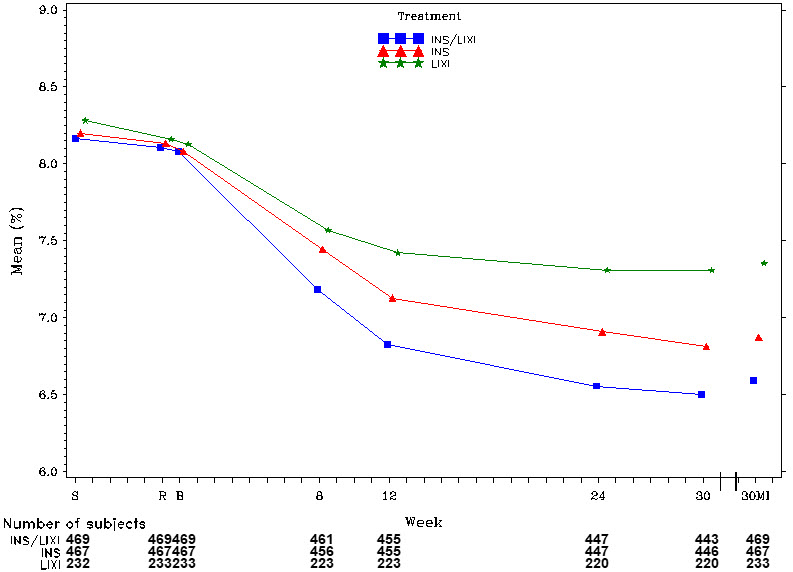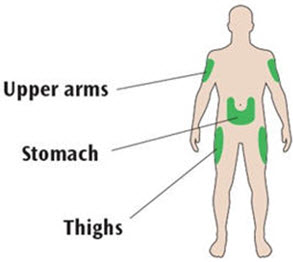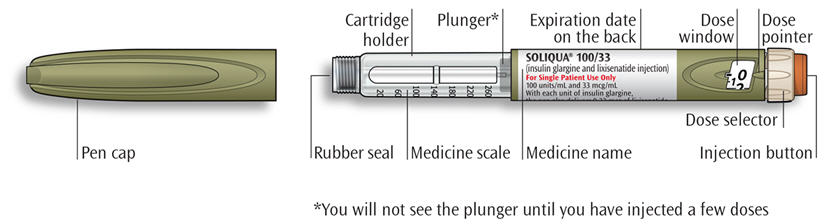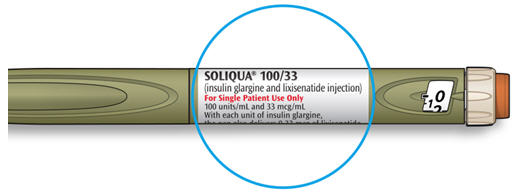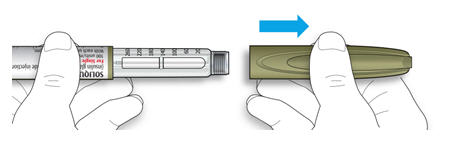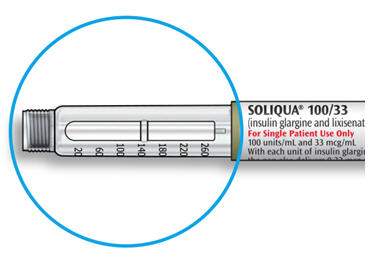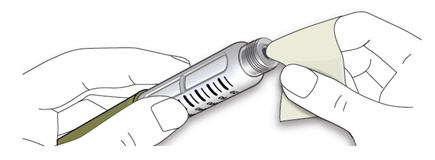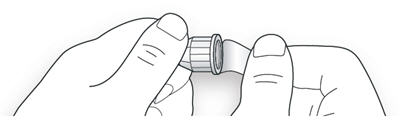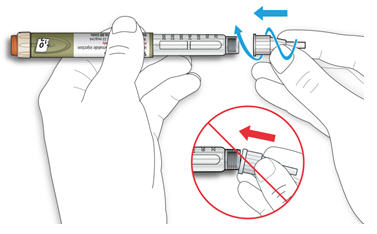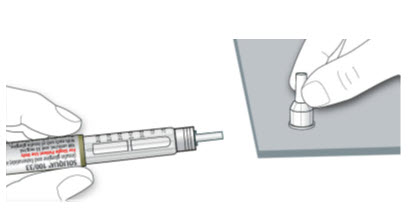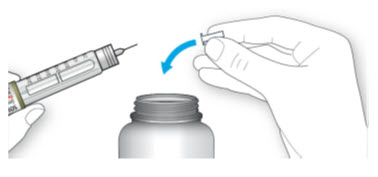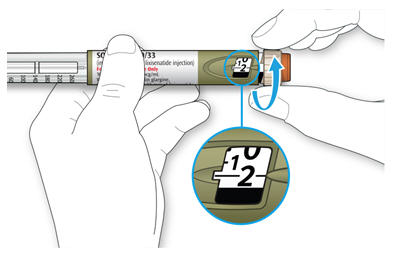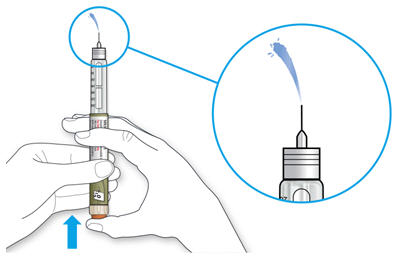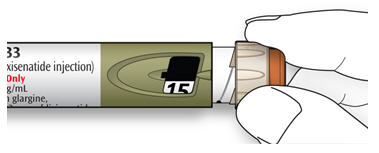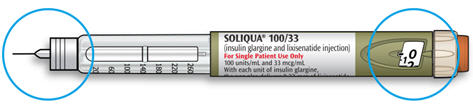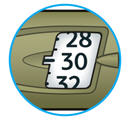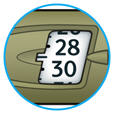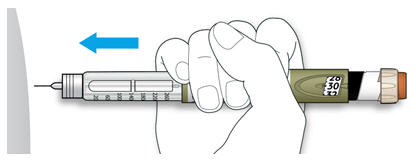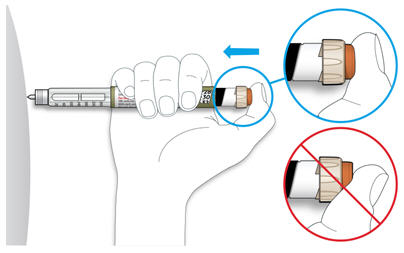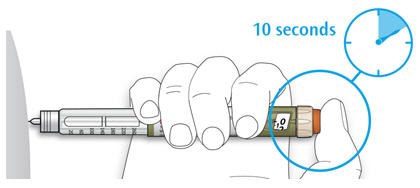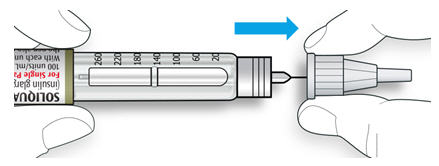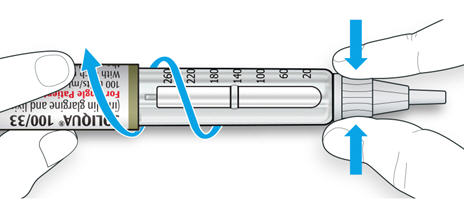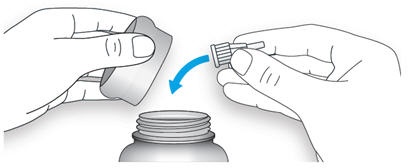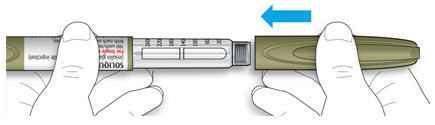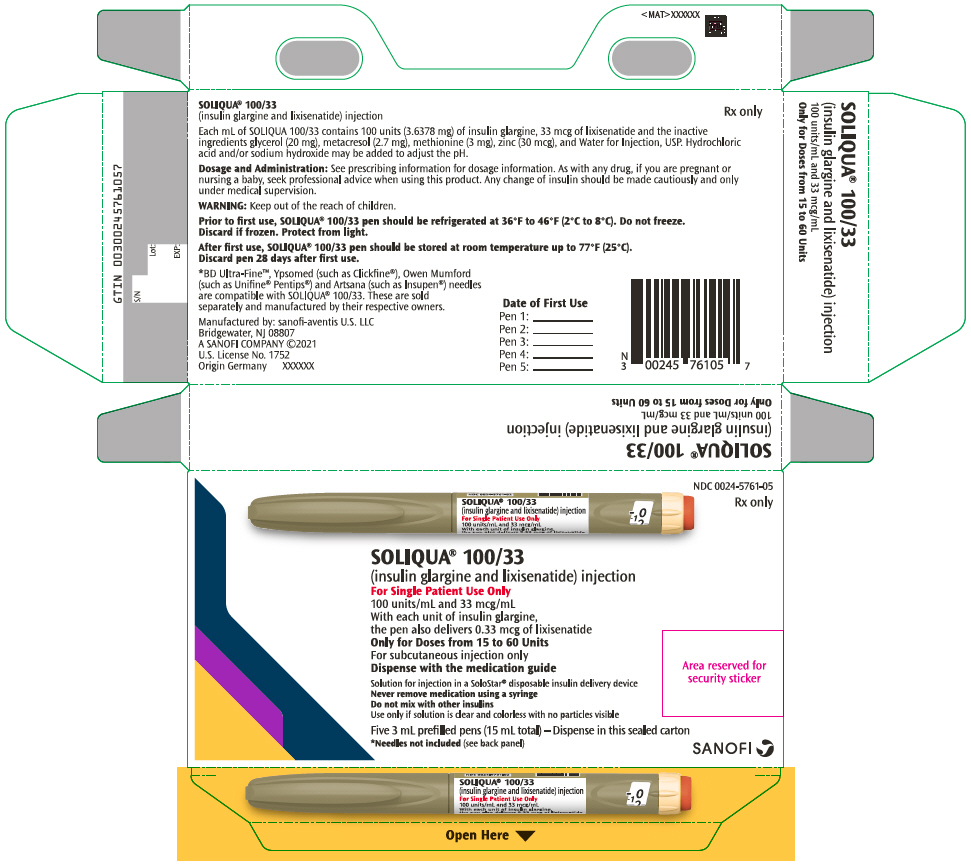 DRUG LABEL: Soliqua 100/33
NDC: 0024-5761 | Form: INJECTION, SOLUTION
Manufacturer: Sanofi-Aventis U.S. LLC
Category: prescription | Type: HUMAN PRESCRIPTION DRUG LABEL
Date: 20250728

ACTIVE INGREDIENTS: INSULIN GLARGINE 100 U/1 mL; LIXISENATIDE 33 ug/1 mL
INACTIVE INGREDIENTS: ZINC CHLORIDE 30 ug/1 mL; METACRESOL 2.7 mg/1 mL; GLYCERIN 20 mg/1 mL; WATER; METHIONINE 3 mg/1 mL; SODIUM HYDROXIDE; HYDROCHLORIC ACID

HIGHLIGHTS OF PRESCRIBING INFORMATION

These highlights do not include all the information needed to use SOLIQUA 100/33 safely and effectively. See full prescribing information for SOLIQUA 100/33.
SOLIQUA® 100/33 (insulin glargine and lixisenatide) injection, for subcutaneous use
Initial U.S. Approval: 2016

RECENT MAJOR CHANGES

Warnings and Precautions, Severe Gastrointestinal Adverse Reactions (5.8) | 5/2025
Warnings and Precautions, Pulmonary Aspiration During General Anesthesia or Deep Sedation (5.13) | 11/2024

1 INDICATIONS AND USAGE

SOLIQUA 100/33 is a combination of insulin glargine, an insulin analog, and lixisenatide, a glucagon-like peptide-1 (GLP-1) receptor agonist, indicated as an adjunct to diet and exercise to improve glycemic control in adults with type 2 diabetes mellitus. (1)

Limitations of Use (1):

- Concomitant use in combination with any other product containing a GLP-1 receptor agonist is not recommended.
- Not recommended for the treatment of diabetic ketoacidosis.
- Has not been studied in combination with prandial insulin.

2 DOSAGE AND ADMINISTRATION

- Inject subcutaneously once a day within the hour prior to the first meal of the day. (2.1)
- SOLIQUA 100/33 pen delivers 15 units to 60 units per injection. (2.1, 2.2)
- Maximum daily dosage is 60 units (60 units of insulin glargine and 20 mcg of lixisenatide). (2.1)
- Discontinue basal insulin or GLP-1 receptor agonist prior to initiation. (2.2)
- In patients naive to basal insulin or to a GLP-1 receptor agonist, currently on less than 30 units of basal insulin, or on a GLP-1 receptor agonist, the recommended starting dosage is 15 units subcutaneously once daily. (2.2)
- In patients inadequately controlled on 30 to 60 units of basal insulin, the starting dosage is 30 units subcutaneously once daily. (2.2)
- See Full Prescribing Information for titration recommendations. (2.3)
- Inject subcutaneously in abdominal area, thigh, or upper arm and rotate injection sites within the same region from one injection to the next to reduce risk of lipodystrophy and localized cutaneous amyloidosis. (2.5)
- Do not administer intravenously, or via an infusion pump. (2.5)
- Do not dilute or mix with any other insulin products or solutions. (2.5)

3 DOSAGE FORMS AND STRENGTHS

Injection: 100 units insulin glargine and 33 mcg lixisenatide per mL in a 3 mL single-patient-use pen. (3)

4 CONTRAINDICATIONS

- During episodes of hypoglycemia. (4)
- Serious hypersensitivity to insulin glargine, lixisenatide, or any of the excipients in SOLIQUA 100/33 (4)

5 WARNINGS AND PRECAUTIONS

- Anaphylaxis and Serious Hypersensitivity Reactions: Severe, life-threatening, and generalized allergic reactions can occur. Instruct patients to discontinue use if a reaction occurs and promptly seek medical attention. (5.1)
- Acute Pancreatitis: Has been observed in patients treated with GLP-1 receptor agonists, including SOLIQUA 100/33. Discontinue if pancreatitis is suspected. (5.2)
- Never share a SOLIQUA 100/33 prefilled pen between patients, even if the needle is changed. (5.3)
- Hyperglycemia or Hypoglycemia with Changes in Insulin Regimen: Make changes to a patient's insulin regimen (e.g., insulin strength, manufacturer, type, injection site or method of administration) under close medical supervision with increased frequency of blood glucose monitoring. (5.4)
- Overdose Due to Medication Errors: SOLIQUA 100/33 contains two drugs. Instruct patients to always check the label before each injection since accidental mix-ups with insulin products can occur. Do not exceed the maximum dose or use with other GLP-1 receptor agonists. (5.5)
- Hypoglycemia: May be life-threatening. Increase frequency of glucose monitoring with changes to insulin dosage, coadministered glucose lowering medications, meal pattern, physical activity; and in patients with renal or hepatic impairment and hypoglycemia unawareness. (5.6)
- Acute kidney injury Due to Volume Depletion: Monitor renal function in patients reporting adverse reactions that could lead to volume depletion. SOLIQUA 100/33 is not recommended in patients with end-stage renal disease. (5.7)
- Severe Gastrointestinal Adverse Reactions: Use has been associated with gastrointestinal adverse reactions, sometimes severe. SOLIQUA 100/33 is not recommended in patients with severe gastroparesis (5.8).
- Immunogenicity: Patients may develop antibodies to insulin glargine and lixisenatide. If there is worsening glycemic control or failure to achieve targeted glycemic control, significant injection-site reactions or allergic reactions, alternative antidiabetic therapy should be considered. (5.9)
- Hypokalemia: May be life-threatening. Monitor potassium levels in patients at risk of hypokalemia and treat if indicated. (5.10)
- Fluid Retention and Heart Failure with Use of PPAR-gamma agonists): Observe for signs and symptoms of heart failure; consider dosage reduction or discontinuation if heart failure occurs. (5.11)
- Acute Gallbladder Disease: If cholelithiasis or cholecystitis are suspected, gallbladder studies are indicated. (5.12)
- Pulmonary Aspiration During General Anesthesia or Deep Sedation: Has been reported in patients receiving GLP-1 receptor agonists undergoing elective surgeries or procedures. Instruct patients to inform healthcare providers of any planned surgeries or procedures.(5.13)

6 ADVERSE REACTIONS

The most common adverse reactions, reported in ≥5% of patients treated with SOLIQUA 100/33 include hypoglycemia, nausea, nasopharyngitis, diarrhea, upper respiratory tract infection, and headache. (6.1)

To report SUSPECTED ADVERSE REACTIONS, contact sanofi-aventis at 1-800-633-1610 or FDA at 1-800-FDA-1088 or www.fda.gov/medwatch.

7 DRUG INTERACTIONS

- Drugs that affect glucose metabolism: Adjustment of SOLIQUA 100/33 dosage may be needed; closely monitor blood glucose. (7.1)
- Antiadrenergic Drugs (e.g., beta-blockers, clonidine, guanethidine, and reserpine): Hypoglycemia signs and symptoms may be reduced. (7.1)
- Effects of delayed gastric emptying on oral medications: Lixisenatide delays gastric emptying which may impact absorption of concomitantly administered oral medications. Oral contraceptives and other medications such as antibiotics and acetaminophen should be taken at least 1 hour prior to SOLIQUA 100/33 administration or 11 hours after. (7.2)

8 USE IN SPECIFIC POPULATIONS

- Pregnancy: SOLIQUA 100/33 should be used during pregnancy only if the potential benefit justifies the potential risk to the fetus. (8.1)

FULL PRESCRIBING INFORMATION

1 INDICATIONS AND USAGE

SOLIQUA 100/33 is a combination of insulin glargine and lixisenatide and is indicated as an adjunct to diet and exercise to improve glycemic control in adults with type 2 diabetes mellitus.

Limitations of Use:

- SOLIQUA 100/33 contains lixisenatide. Coadministration with any other product containing lixisenatide or another glucagon-like peptide-1 (GLP-1) receptor agonist is not recommended [see Warnings and Precautions (5.5)].
- SOLIQUA 100/33 is not recommended for the treatment of diabetic ketoacidosis.
- SOLIQUA 100/33 has not been studied in combination with prandial insulin.

2 DOSAGE AND ADMINISTRATION

2.1 Important Dosage Information

- SOLIQUA 100/33 is a combination of insulin glargine and lixisenatide.
- Administer SOLIQUA 100/33 subcutaneously once a day within the hour prior to the first meal of the day.
- The SOLIQUA 100/33 pen delivers doses from 15 to 60 units in a single injection. Table 1 presents the units of insulin glargine and the micrograms of lixisenatide in each dosage of SOLIQUA 100/33 [see Dosage and Administration (2.2)].
- The maximum dose of SOLIQUA 100/33 is 60 units daily (60 units insulin glargine and 20 mcg lixisenatide) [see Warnings and Precautions (5.5)].

2.2 Recommended Starting Dose

In patients naive to basal insulin or to a GLP-1 receptor agonist, currently on a GLP-1 receptor agonist or currently on less than 30 units of basal insulin daily:

- Discontinue therapy with basal insulin or a GLP-1 receptor agonist prior to initiation of SOLIQUA 100/33.
- The recommended starting dosage of SOLIQUA 100/33 is 15 units (15 units insulin glargine and 5 mcg lixisenatide) given subcutaneously once daily.

In patients currently on 30 to 60 units of basal insulin daily, with or without a GLP-1 receptor agonist:

- Discontinue therapy with basal insulin or GLP-1 receptor agonist prior to initiation of SOLIQUA 100/33.
- The recommended starting dosage of SOLIQUA 100/33 is 30 units (30 units insulin glargine and 10 mcg lixisenatide) given subcutaneously once daily.

Table 1: Units of Insulin Glargine and Micrograms of Lixisenatide in Each Dosage of SOLIQUA 100/33
SOLIQUA 100/33 (dose window display) [The dose window on the SOLIQUA 100/33 pen displays numbers for the even units and displays lines for the odd units.] | Insulin glargine component dose | Lixisenatide component dose | Comment
2 | --- | --- | Safety test dose – not for injection
15 | 15 units | 5 mcg | Recommended starting dosage for patients naive to basal insulin or GLP-1 receptor agonist, currently on GLP-1 receptor agonist, or currently on less than 30 units of basal insulin daily
16 | 16 units | 5.3 mcg
17 | 17 units | 5.7 mcg
18 | 18 units | 6 mcg
19 | 19 units | 6.3 mcg
20 | 20 units | 6.7 mcg
21 | 21 units | 7 mcg
22 | 22 units | 7.3 mcg
23 | 23 units | 7.7 mcg
24 | 24 units | 8 mcg
25 | 25 units | 8.3 mcg
26 | 26 units | 8.7 mcg
27 | 27 units | 9 mcg
28 | 28 units | 9.3 mcg
29 | 29 units | 9.7 mcg
30 | 30 units | 10 mcg | Recommended starting dosage for patients currently on 30 to 60 units of basal insulin daily, with or without a GLP-1 receptor agonist:
31 | 31 units | 10.3 mcg
32 | 32 units | 10.7 mcg
33 | 33 units | 11 mcg
34 | 34 units | 11.3 mcg
35 | 35 units | 11.7 mcg
36 | 36 units | 12 mcg
37 | 37 units | 12.3 mcg
38 | 38 units | 12.7 mcg
39 | 39 units | 13 mcg
40 | 40 units | 13.3 mcg
41 | 41 units | 13.7 mcg
42 | 42 units | 14 mcg
43 | 43 units | 14.3 mcg
44 | 44 units | 14.7 mcg
45 | 45 units | 15 mcg
46 | 46 units | 15.3 mcg
47 | 47 units | 15.7 mcg
48 | 48 units | 16 mcg
49 | 49 units | 16.3 mcg
50 | 50 units | 16.7 mcg
51 | 51 units | 17 mcg
52 | 52 units | 17.3 mcg
53 | 53 units | 17.7 mcg
54 | 54 units | 18 mcg
55 | 55 units | 18.3 mcg
56 | 56 units | 18.7 mcg
57 | 57 units | 19 mcg
58 | 58 units | 19.3 mcg
59 | 59 units | 19.7 mcg
60 | 60 units | 20 mcg | Maximum daily dosage [see Warnings and Precautions (5.5)]

2.3 Titration of SOLIQUA 100/33

- After starting with the recommended dosage of SOLIQUA 100/33, [see Dosage and Administration (2.2)], titrate the dosage upwards or downwards by two to four units (see Table 2) every week based on the patient's metabolic needs, blood glucose monitoring results, and glycemic control goal until the desired fasting plasma glucose is achieved.
- To minimize the risk of hypoglycemia or hyperglycemia, additional titration may be needed with changes in physical activity, meal patterns (i.e., macronutrient content or timing of food intake), or renal or hepatic function; during acute illness; or when used with other medications [see Warnings and Precautions (5.4) and Drug Interactions (7)].

Table 2: Recommended Titration of SOLIQUA 100/33 (Every Week) [The recommended SOLIQUA 100/33 dosage is between 15 to 60 units (see Table 1).]
Self-Monitored Fasting Plasma Glucose | SOLIQUA 100/33 Dosage Adjustment
Above target range | +2 units (2 units of insulin glargine and 0.66 mcg of lixisenatide) to +4 units (4 units of insulin glargine and 1.32 mcg of lixisenatide)
Within target range | 0 units
Below target range | -2 units (2 units of insulin glargine and 0.66 mcg of lixisenatide) to -4 units (4 units of insulin glargine and 1.32 mcg of lixisenatide)

2.4 Missed Doses

Instruct patients who miss a dose of SOLIQUA 100/33 to resume the once-daily regimen as prescribed with the next scheduled dose. Do not administer an extra dose or increase the dose to make up for the missed dose.

2.5 Important Administration Instructions

- The SOLIQUA 100/33 prefilled pen is for single-patient-use only [see Warnings and Precautions (5.3)].
- Train patients on proper use and injection technique before initiating SOLIQUA 100/33.
- Always check the SOLIQUA 100/33 label before administration [see Warnings and Precautions (5.5)].
- Visually inspect for particulate matter and discoloration prior to administration. Only use SOLIQUA 100/33 if the solution is clear and colorless to almost colorless.
- Inject SOLIQUA 100/33 subcutaneously into the abdominal area, thigh, or upper arm.
- Rotate injection sites within the same region from one injection to the next to reduce the risk of lipodystrophy and localized cutaneous amyloidosis. Do not inject into areas of lipodystrophy or localized cutaneous amyloidosis [see Warnings and Precautions (5.2), Adverse Reactions (6)].
- During changes to a patient's insulin regimen, increase the frequency of blood glucose monitoring [see Warnings and Precautions (5.4)].
- Do not administer intravenously or via an insulin pump.
- Use SOLIQUA 100/33 with caution in patients with visual impairment who may rely on audible clicks to dial their dose.
- The SOLIQUA 100/33 pen dials in 1-unit increments.
- Do not dilute or mix SOLIQUA 100/33 with any other insulin or solution.
- Do not split the dose of SOLIQUA 100/33.

3 DOSAGE FORMS AND STRENGTHS

SOLIQUA 100/33 is a clear, colorless to almost colorless solution available as:

Injection: 100 units of insulin glargine and 33 mcg of lixisenatide per mL in a 3 mL prefilled, disposable, single-patient-use SoloStar® pen.

4 CONTRAINDICATIONS

SOLIQUA 100/33 is contraindicated:

- During episodes of hypoglycemia [see Warnings and Precautions (5.6)].
- In patients with serious hypersensitivity to insulin glargine, lixisenatide, or any of the excipients in SOLIQUA 100/33. Hypersensitivity reactions including anaphylaxis have occurred with both lixisenatide and insulin glargine [see Warnings and Precautions (5.1) and Adverse Reactions (6.1)].

5 WARNINGS AND PRECAUTIONS

5.1 Anaphylaxis and Serious Hypersensitivity Reactions

In clinical trials of lixisenatide there have been cases of anaphylaxis (frequency of 0.1% or 10 cases per 10,000 patient-years) and other serious hypersensitivity reactions including angioedema. Severe, life-threatening, generalized allergic reactions, including anaphylaxis, generalized skin reactions, angioedema, bronchospasm, hypotension, and shock can occur with insulins, including insulin glargine. There have been postmarketing reports of serious hypersensitivity reactions, including anaphylactic reactions and angioedema, in patients treated with SOLIQUA 100/33 [see Adverse Reactions (6.1)].

Inform and closely monitor patients with a history of anaphylaxis or angioedema with another GLP-1 receptor agonist for allergic reactions, because it is unknown whether such patients will be predisposed to anaphylaxis with SOLIQUA 100/33. SOLIQUA 100/33 is contraindicated in patients with known serious hypersensitivity to lixisenatide or insulin glargine [see Contraindications (4)]. If a hypersensitivity reaction occurs, the patient should discontinue SOLIQUA 100/33 and promptly seek medical attention.

5.2 Acute Pancreatitis

Acute pancreatitis, including fatal and non-fatal hemorrhagic or necrotizing pancreatitis, has been observed in patients treated with GLP-1 receptor agonists [see Adverse Reactions (6)].

After initiation of SOLIQUA 100/33, observe patients carefully for signs and symptoms of pancreatitis (including persistent severe abdominal pain, sometimes radiating to the back and which may or may not be accompanied by vomiting). If pancreatitis is suspected, discontinue SOLIQUA 100/33 and initiate appropriate management.

5.3 Never Share a SOLIQUA 100/33 Prefilled Pen Between Patients

SOLIQUA 100/33 prefilled pens must never be shared between patients, even if the needle is changed. Sharing of the pen poses a risk for transmission of blood-borne pathogens.

5.4 Hyperglycemia or Hypoglycemia with Changes in Insulin Regimen

Changes in insulin regimen (e.g., insulin strength, manufacturer, type, injection site or method of administration) may affect glycemic control and predispose to hypoglycemia [see Warnings and Precautions (5.6)] or hyperglycemia. Repeated insulin injections into areas of lipodystrophy or localized cutaneous amyloidosis have been reported to result in hyperglycemia; and a sudden change in the injection site (to unaffected area) has been reported to result in hypoglycemia [see Adverse Reactions (6)].

Make any changes to a patient's insulin regimen under close medical supervision with increased frequency of blood glucose monitoring. Advise patients who have repeatedly injected into areas of lipodystrophy or localized cutaneous amyloidosis to change the injection site to unaffected areas and closely monitor for hypoglycemia. Adjustments in concomitant oral antidiabetic treatment may be needed. When converting from basal insulin therapy or a GLP-1 receptor agonist to SOLIQUA 100/33 follow dosing recommendations [see Dosage and Administration (2.2, 2.3)].

5.5 Overdose Due to Medication Errors

SOLIQUA 100/33 contains two drugs: insulin glargine and lixisenatide. Administration of more than 60 units of SOLIQUA 100/33 daily can result in overdose of the lixisenatide component. Do not exceed the 20-mcg maximum recommended dose of lixisenatide or use with other GLP-1 receptor agonists.

Accidental mix-ups between insulin products have been reported. To avoid medication errors between SOLIQUA 100/33 and other insulins, instruct patients to always check the insulin label before each injection.

5.6 Hypoglycemia

Hypoglycemia is the most common adverse reaction associated with insulin-containing products, including SOLIQUA 100/33 [see Adverse Reactions (6.1)]. Severe hypoglycemia can cause seizures, may be life-threatening or cause death. Hypoglycemia can impair concentration ability and reaction time; this may place an individual and others at risk in situations where these abilities are important (e.g., driving or operating other machinery). SOLIQUA 100/33 (an insulin-containing product), or any insulin, should not be used during episodes of hypoglycemia [see Contraindications (4)].

Hypoglycemia can happen suddenly, and symptoms may differ in each individual and change over time in the same individual. Symptomatic awareness of hypoglycemia may be less pronounced in patients with longstanding diabetes, in patients with diabetic nerve disease, in patients using medications that block the sympathetic nervous system (e.g., beta-blockers) [see Drug Interactions (7.1)], or in patients who experience recurrent hypoglycemia.

Risk Factors for Hypoglycemia

The risk of hypoglycemia generally increases with intensity of glycemic control. The risk of hypoglycemia after an injection is related to the duration of action of the insulin and, in general, is highest when the glucose lowering effect of the insulin is maximal. As with all insulin-containing preparations, the glucose lowering effect time course of SOLIQUA 100/33 may vary in different individuals or at different times in the same individual and depends on many conditions, including the area of injection as well as the injection-site blood supply and temperature [see Clinical Pharmacology (12.2)].

Other factors which may increase the risk of hypoglycemia include changes in meal pattern (e.g., macronutrient content or timing of meals), changes in level of physical activity, or changes to coadministered medication [see Drug Interactions (7.1)]. Patients with renal or hepatic impairment may be at higher risk of hypoglycemia [see Use in Specific Populations (8.6, 8.7)].

Risk Mitigation Strategies for Hypoglycemia

Patients and caregivers must be educated to recognize and manage hypoglycemia. Self-monitoring of blood glucose plays an essential role in the prevention and management of hypoglycemia. In patients at higher risk for hypoglycemia and patients who have reduced symptomatic awareness of hypoglycemia, increased frequency of blood glucose monitoring is recommended.

The long-acting effect of insulin glargine may delay recovery from hypoglycemia.

5.7 Acute Kidney Injury Due to Volume Depletion

There have been postmarketing reports of acute kidney injury, in some cases requiring hemodialysis, in patients treated with GLP-1 receptor agonists [see Adverse Reactions (6.3)]. The majority of the reported events occurred in patients who experienced gastrointestinal reactions leading to dehydration such as nausea, vomiting, or diarrhea [see Adverse Reactions (6.1)]. Monitor renal function in patients reporting adverse reactions to SOLIQUA 100/33 that could lead to volume depletion, especially during dosage initiation and escalation of SOLIQUA 100/33.SOLIQUA 100/33 is not recommended in patients with end-stage renal disease [see Use in Specific Populations (8.6)].

5.8 Severe Gastrointestinal Adverse Reactions

Use of GLP-1 receptor agonists, including SOLIQUA 100/33, has been associated with gastrointestinal adverse reactions, sometimes severe [see Adverse Reactions (6.)]. SOLIQUA 100/33 is not recommended in patients with severe gastroparesis.

5.9 Immunogenicity

Patients may develop antibodies to insulin and lixisenatide following treatment. A pooled analysis of studies of lixisenatide-treated patients showed that 70% were antibody positive at Week 24. In the subset of patients (2.4%) with the highest antibody concentrations (>100 nmol/L), an attenuated glycemic response was observed. A higher incidence of allergic reactions and injection-site reactions occurred in antibody positive patients [see Warnings and Precautions (5.1), Adverse Reactions (6.2)].

If there is worsening glycemic control or failure to achieve targeted glycemic control, significant injection-site reactions or allergic reactions, alternative antidiabetic therapy should be considered.

5.10 Hypokalemia

All insulin-containing products, including SOLIQUA 100/33, cause a shift in potassium from the extracellular to intracellular space, possibly leading to hypokalemia. Untreated hypokalemia may cause respiratory paralysis, ventricular arrhythmia, and death. Monitor potassium levels in patients at risk for hypokalemia if indicated (e.g., patients using potassium-lowering medications, patients taking medications sensitive to serum potassium concentrations).

5.11 Fluid Retention and Heart Failure with Concomitant Use of PPAR-gamma Agonists

Thiazolidinediones (TZDs), which are peroxisome proliferator-activated receptor (PPAR)-gamma agonists, can cause dose-related fluid retention, particularly when used in combination with insulin-containing products, including SOLIQUA 100/33. Fluid retention may lead to or exacerbate heart failure. Patients treated with SOLIQUA 100/33 and a PPAR-gamma agonist should be observed for signs and symptoms of heart failure. If heart failure develops, it should be managed according to current standards of care, and discontinuation or dose reduction of the PPAR-gamma agonist must be considered.

5.12 Acute Gallbladder Disease

Acute events of gallbladder disease such as cholelithiasis or cholecystitis have been reported in GLP-1 receptor agonist trials and postmarketing. In a cardiovascular outcomes trial, cholelithiasis occurred in 0.4% of lixisenatide-treated patients versus 0.2% in placebo-treated patients and acute cholecystitis in 0.3% of lixisenatide-treated patients versus 0.2% in placebo-treated patients. If cholelithiasis is suspected, gallbladder studies and appropriate clinical follow-up are indicated.

5.13 Pulmonary Aspiration During General Anesthesia or Deep Sedation

SOLIQUA 100/33 delays gastric emptying [see Clinical Pharmacology (12.1)]. There have been rare postmarketing reports of pulmonary aspiration in patients receiving GLP-1 receptor agonists undergoing elective surgeries or procedures requiring general anesthesia or deep sedation who had residual gastric contents despite reported adherence to preoperative fasting recommendations.

Available data are insufficient to inform recommendations to mitigate the risk of pulmonary aspiration during general anesthesia or deep sedation in patients taking SOLIQUA 100/33, including whether modifying preoperative fasting recommendations or temporarily discontinuing SOLIQUA 100/33 could reduce the incidence of retained gastric contents. Instruct patients to inform healthcare providers prior to any planned surgeries or procedures if they are taking SOLIQUA 100/33.

6 ADVERSE REACTIONS

The following adverse reactions are discussed elsewhere:

- Anaphylaxis and Serious Hypersensitivity Reactions [see Warnings and Precautions (5.1)]
- Acute Pancreatitis [see Warnings and Precautions (5.2)]
- Hypoglycemia [see Warnings and Precautions (5.6)]
- Acute Kidney Injury Due to Volume Depletion [see Warnings and Precautions (5.7)]
- Severe Gastrointestinal Adverse Reactions [see Warnings and Precautions (5.8)]
- Hypokalemia [see Warnings and Precautions (5.10)]
- Acute Gallbladder Disease [see Warnings and Precautions (5.12)]
- Pulmonary Aspiration During General Anesthesia or Deep Sedation [see Warnings and Precautions (5.13)]

6.1 Clinical Trials Experience

Because clinical trials are conducted under widely varying conditions, adverse reaction rates observed in clinical trials of a drug cannot be directly compared to rates in the clinical trial of another drug and may not reflect the rates observed in practice.

The safety of SOLIQUA 100/33 (n=834, with a mean treatment duration of 203 days) has been evaluated in two clinical studies (30 weeks duration) in type 2 diabetes patients. The studies, Study A and B [see Clinical Studies (14)], had the following characteristics: mean age was approximately 59 years; approximately 50% were male, 90% were Caucasian, 6% were Black or African American, and 18% were Hispanic. The mean duration of diabetes was 10.3 years, mean HbA1c at screening for Study A was 8.2 and Study B was 8.5. The mean BMI at baseline was 32 kg/m^2. Baseline eGFR was ≥60 mL/min in 87.2% of the pooled study population and mean baseline eGFR was 83.0 mL/min/1.73 m^2.

Table 3: Adverse Reactions Occurring in ≥5% of SOLIQUA 100/33–Treated Patients with Type 2 Diabetes Mellitus from Two Pooled Clinical Trials
 | SOLIQUA 100/33, % (n=834)
Nausea | 10.0
Nasopharyngitis | 7.0
Diarrhea | 7.0
Upper respiratory tract infection | 5.5
Headache | 5.4

Hypoglycemia

Hypoglycemia is the most commonly observed adverse reaction in patients using insulin, and insulin-containing products including SOLIQUA 100/33 [see Warnings and Precautions (5.6)]. The rates of reported hypoglycemia depend on the definition of hypoglycemia used, diabetes type, insulin dose, intensity of glucose control, background therapies, and other intrinsic and extrinsic patient factors. For these reasons, comparing rates of hypoglycemia in clinical trials for SOLIQUA 100/33 with the incidence of hypoglycemia for other products may be misleading and also, may not be representative of hypoglycemia rates that will occur in clinical practice.

In the SOLIQUA 100/33 program, severe hypoglycemia was defined as an event requiring assistance of another person to actively administer carbohydrate, glucagon, or other resuscitative actions and documented symptomatic hypoglycemia was defined as an event with typical symptoms of hypoglycemia accompanied by a self-monitored plasma glucose value equal to or less than 70 mg/dL (see Table 4).

No clinically important differences in risk of severe hypoglycemia between SOLIQUA 100/33 and comparators were observed in clinical trials.

Table 4: Hypoglycemic Episodes in SOLIQUA 100/33-Treated Patients with T2DM
 | SOLIQUA 100/33 Study A N=469 | SOLIQUA 100/33 Study B N=365
Severe symptomatic hypoglycemia [Defined as an event requiring assistance of another person to actively administer carbohydrate, glucagon, or other resuscitative actions.] (%) | 0 | 1.1
Hypoglycemia (self-monitored plasma glucose <54 mg/dL) (%) | 8.1 | 17.8

Gastrointestinal Adverse Reactions

Gastrointestinal adverse reactions are the most commonly observed adverse reaction in patients using lixisenatide. Gastrointestinal adverse reactions occur more frequently at the beginning of SOLIQUA 100/33 therapy. Gastrointestinal adverse reactions including nausea, diarrhea, vomiting, constipation, dyspepsia, gastritis, abdominal pain, flatulence, gastroesophageal reflux disease, abdominal distension, and decreased appetite have been reported in patients treated with SOLIQUA 100/33.

In Study A, vomiting was 6.4% in the lixisenatide-treated patients versus 3.2% in the SOLIQUA 100/33–treated patients and 1.5% in the insulin glargine–treated patients; nausea was 24% in the lixisenatide-treated patients versus 9.6% in the SOLIQUA 100/33–treated patients, and 3.6% in the insulin glargine–treated patients.

Lipodystrophy

Administration of insulin subcutaneously, including SOLIQUA 100/33, has resulted in lipoatrophy (depression in the skin) or lipohypertrophy (enlargement or thickening of tissue) in some patients [see Dosage and Administration (2.5)].

Anaphylaxis and Hypersensitivity

Lixisenatide

In the lixisenatide development program anaphylaxis cases were adjudicated. Anaphylaxis was defined as a skin or mucosal lesion of acute onset associated with at least 1 other organ system involvement. Symptoms such as hypotension, laryngeal edema or severe bronchospasm could be present but were not required for the case definition. More cases adjudicated as meeting the definition for anaphylaxis occurred in lixisenatide-treated patients (incidence rate of 0.2% or 16 cases per 10,000 patient years) than placebo-treated patient (incidence rate of 0.1% or 7 cases per 10,000 patient years).

Allergic reactions (such as anaphylactic reaction, angioedema, and urticaria) adjudicated as possibly related to the study medication were observed more frequently in lixisenatide-treated patients (0.4%) than placebo-treated patients (0.2%) [see Warnings and Precautions (5.1)].

Insulin glargine

Severe, life-threatening, generalized allergy, including anaphylaxis, generalized skin reactions, angioedema, bronchospasm, hypotension, and shock may occur with any insulin, including SOLIQUA 100/33, and may be life-threatening.

Pancreatitis

In clinical trials of lixisenatide there were 21 cases of pancreatitis among lixisenatide-treated patients and 14 cases in comparator-treated patients (incidence rate of 21 vs 17 per 10,000 patient-years). Lixisenatide cases were reported as acute pancreatitis (n=3), pancreatitis (n=12), chronic pancreatitis (n=5), and edematous pancreatitis (n=1). Some patients had risk factors for pancreatitis, such as a history of cholelithiasis or alcohol abuse.

Acute Gallbladder Disease

In a cardiovascular outcomes trial, cholelithiasis occurred in 0.4% of lixisenatide-treated patients versus 0.2% in placebo-treated patients and acute cholecystitis in 0.3% of lixisenatide-treated patients versus 0.2% in placebo-treated patients.

Injection-Site Reactions

As with any insulin or GLP-1 receptor agonist–containing product, patients taking SOLIQUA 100/33 may experience injection-site reactions, including injection-site hematoma, pain, hemorrhage, erythema, nodules, swelling, discoloration, pruritus, warmth, and injection-site mass. In the clinical program the proportion of injection-site reactions occurring in patients treated with SOLIQUA 100/33 was 1.7%.

Insulin Initiation and Intensification of Glucose Control

Intensification or rapid improvement in glucose control has been associated with a transitory, reversible ophthalmologic refraction disorder, worsening of diabetic retinopathy, and acute painful peripheral neuropathy. However, long-term glycemic control decreases the risk of diabetic retinopathy and neuropathy.

Peripheral Edema

Some patients taking insulin glargine, a component of SOLIQUA 100/33 have experienced sodium retention and edema, particularly if previously poor metabolic control is improved by intensified insulin therapy.

Weight Gain

Weight gain can occur with insulin-containing products, including SOLIQUA 100/33, and has been attributed to the anabolic effects of insulin.

6.2 Immunogenicity

SOLIQUA 100/33

As with all therapeutic proteins, there is potential for immunogenicity. The detection of antibody formation is highly dependent on the sensitivity and specificity of the assay. Additionally, the observed incidence of antibody (including neutralizing antibody) positivity in an assay may be influenced by several factors including assay methodology, sample handling, timing of sample collection, concomitant medications, and underlying disease. For these reasons, comparison of the incidence of antibodies to SOLIQUA 100/33 in the studies described below with the incidence of antibodies in other studies or to other products may be misleading.

After 30 weeks of treatment with SOLIQUA 100/33 in two phase 3 trials, the incidence of formation of anti-insulin glargine antibodies was 21.0% and 26.2%. In approximately 93% of the patients, anti-insulin glargine antibodies showed cross-reactivity to human insulin. The incidence of formation of anti-lixisenatide antibodies was approximately 43%.

Lixisenatide

In the pool of 9 placebo-controlled studies, 70% of patients exposed to lixisenatide tested positive for anti-lixisenatide antibodies during the trials. In the subset of patients (2.4%) with the highest antibody concentrations (>100 nmol/L), an attenuated glycemic response was observed. A higher incidence of allergic reactions and injection-site reactions occurred in antibody positive patients [see Warnings and Precautions (5.9)].

Anti-lixisenatide antibody characterization studies have demonstrated the potential for development of antibodies cross-reactive with endogenous GLP-1 and glucagon, but their incidence has not been fully determined and the clinical significance of these antibodies is not currently known.

No information regarding the presence of neutralizing antibodies is currently available.

6.3 Postmarketing Experience

The following additional adverse reactions have been identified during post approval use. Because these reactions are reported voluntarily from a population of uncertain size, it is not always possible to reliably estimate their frequency or establish a causal relationship to drug exposure.

Insulin glargine:

Localized cutaneous amyloidosis at the injection site has occurred with insulins. Hyperglycemia has been reported with repeated insulin injections into areas of localized cutaneous amyloidosis; hypoglycemia has been reported with a sudden change to an unaffected injection site;

Lixisenatide:

Gastrointestinal: acute pancreatitis, hemorrhagic and necrotizing pancreatitis, ileus

Hepatobiliary: cholecystitis, cholelithiasis requiring cholecystectomy

Neurologic: dysgeusia, dysesthesia

Pulmonary: pulmonary aspiration has occurred in patients receiving GLP-1 receptor agonists undergoing elective surgeries or procedures requiring general anesthesia or deep sedation.

Renal: acute renal failure or worsening of chronic renal failure, sometimes requiring hemodialysis

Skin and Subcutaneous Tissue: alopecia.

7 DRUG INTERACTIONS

7.1 Medications that Can Affect Glucose Metabolism

A number of medications affect glucose metabolism and may require dose adjustment of SOLIQUA 100/33 and particularly close monitoring.

Drugs That May Increase the Risk of Hypoglycemia
Drugs: | Antidiabetic agents, ACE inhibitors, angiotensin II receptor blocking agents, disopyramide, fibrates, fluoxetine, monoamine oxidase inhibitors, pentoxifylline, pramlintide, salicylates, somatostatin analogs (e.g., octreotide), and sulfonamide antibiotics.
Intervention: | Dose reductions and increased frequency of glucose monitoring may be required when SOLIQUA 100/33 is coadministered with these drugs.
Drugs That May Decrease the Blood Glucose Lowering Effect of SOLIQUA 100/33
Drugs: | Atypical antipsychotics (e.g., olanzapine and clozapine), corticosteroids, danazol, diuretics, estrogens, glucagon, isoniazid, niacin, oral contraceptives, phenothiazines, progestogens (e.g., in oral contraceptives), protease inhibitors, somatropin, sympathomimetic agents (e.g., albuterol, epinephrine, terbutaline), and thyroid hormones.
Intervention: | Dose increases and increased frequency of glucose monitoring may be required when SOLIQUA 100/33 is coadministered with these drugs.
Drugs That May Increase or Decrease the Blood Glucose Lowering Effect of SOLIQUA 100/33
Drugs: | Alcohol, beta-blockers, clonidine, and lithium salts. Pentamidine may cause hypoglycemia, which may sometimes be followed by hyperglycemia.
Intervention: | Dose adjustment and increased frequency of glucose monitoring may be required when SOLIQUA 100/33 is coadministered with these drugs.
Drugs That May Blunt Signs and Symptoms of Hypoglycemia
Drugs: | Beta-blockers, clonidine, guanethidine, and reserpine.
Intervention: | Increased frequency of glucose monitoring may be required when SOLIQUA 100/33 is coadministered with these drugs.

7.2 Effects of Delayed Gastric Emptying on Oral Medications

Lixisenatide-containing products, including SOLIQUA 100/33, delay gastric emptying which may reduce the rate of absorption of orally administered medications. Use caution when coadministering oral medications that have a narrow therapeutic ratio or that require careful clinical monitoring. These medications should be adequately monitored when concomitantly administered with lixisenatide. If such medications are to be administered with food, patients should be advised to take them with a meal or snack when lixisenatide is not administered.

- Antibiotics, acetaminophen, or other medications that are particularly dependent on threshold concentrations for efficacy or for which a delay in effect is undesirable should be administered at least 1 hour before SOLIQUA 100/33 injection [see Clinical Pharmacology (12.3)].
- Oral contraceptives should be taken at least 1 hour before SOLIQUA 100/33 administration or 11 hours after [see Clinical Pharmacology (12.3)].

8 USE IN SPECIFIC POPULATIONS

8.1 Pregnancy

Risk Summary

Based on animal reproduction studies, there may be risks to the fetus from exposure to lixisenatide, a component of SOLIQUA 100/33, during pregnancy. SOLIQUA 100/33 should be used during pregnancy only if the potential benefit justifies the potential risk to the fetus.

The limited available data with SOLIQUA 100/33 and lixisenatide in pregnant women is not sufficient to inform a drug-associated risk of major birth defects and miscarriage. Published studies with insulin glargine use during pregnancy have not reported a clear association with insulin glargine and major birth defect or miscarriage risk [see Data]. There are risks to the mother and fetus associated with poorly controlled diabetes in pregnancy [see Clinical Considerations].

Lixisenatide administered to pregnant rats and rabbits during organogenesis was associated with visceral closure and skeletal defects at systemic exposures that decreased maternal food intake and weight gain during gestation, and that are 1-time and 6-times higher than the 20 mcg/day highest clinical dose, respectively, based on plasma AUC [see Data].

The estimated background risk of major birth defects is 6%–10% in women with pregestational diabetes with a HbA1c >7 and has been reported to be as high as 20%–25% in women with a HbA1c >10. The estimated background risk of miscarriage for the indicated population is unknown. In the U.S. general population, the estimated background risk of major birth defects and miscarriage in clinically recognized pregnancies is 2%–4% and 15%–20%, respectively.

Clinical considerations

Disease-associated maternal and/or embryo/fetal risk

Poorly controlled diabetes in pregnancy increases the maternal risk for diabetic ketoacidosis, pre-eclampsia, spontaneous abortions, preterm delivery, and delivery complications. Poorly controlled diabetes increases the fetal risk for major birth defects, still birth, and macrosomia related morbidity.

Data

Human data

Insulin glargine

Published data do not report a clear association with insulin glargine and major birth defects, miscarriage, or adverse maternal or fetal outcomes when insulin glargine is used during pregnancy. However, these studies cannot definitely establish the absence of any risk because of methodological limitations including small sample size and some lacking comparator groups.

Animal data

Animal reproduction studies were not conducted with the combined products in SOLIQUA 100/33. The following data are based on studies conducted with the individual components of SOLIQUA 100/33.

Lixisenatide

In pregnant rats receiving twice daily subcutaneous doses of 2.5, 35, or 500 mcg/kg during organogenesis (gestation day 6 to 17), fetuses were present with visceral closure defects (e.g., microphthalmia, bilateral anophthalmia, diaphragmatic hernia) and stunted growth. Impaired ossification associated with skeletal malformations (e.g., bent limbs, scapula, clavicle, and pelvis) were observed at ≥2.5 mcg/kg/dose, resulting in systemic exposure that is 1-time the 20 mcg/day clinical dose, based on plasma AUC. Decreases in maternal body weight, food consumption, and motor activity were observed concurrent with the adverse fetal findings, which confounds the interpretation of relevance of these malformations to the human risk assessment. Placental transfer of lixisenatide to developing rat fetuses is low with a concentration ratio in fetal/maternal plasma of 0.1%.

In pregnant rabbits receiving twice daily subcutaneous doses of 2.5, 25, 250 mcg/kg during organogenesis (gestation day 6 to 18), fetuses were present with multiple visceral and skeletal malformations, including closure defects, at ≥5 mcg/kg/day or systemic exposures that are 6-times the 20 mcg/day highest clinical dose, based on plasma AUC. Decreases in maternal body weight, food consumption, and motor activity were observed concurrent with the fetal findings, which confounds the interpretation of relevance of these malformations to the human risk assessment. Placental transfer of lixisenatide to developing rabbit fetuses is low with a concentration ratio in fetal/maternal plasma of ≤0.3%. In a second study in pregnant rabbits, no drug-related malformations were observed from twice daily subcutaneous doses of 0.15, 1.0, and 2.5 mcg/kg administered during organogenesis, resulting in systemic exposures up to 9-times the clinical exposure at 20 mcg/day, based on plasma AUC.

In pregnant rats given twice daily subcutaneous doses of 2, 20, or 200 mcg/kg from gestation day 6 through lactation, decreases in maternal body weight, food consumption, and motor activity were observed at all doses. Skeletal malformations and increased pup mortality were observed at 400 mcg/kg/day, which is approximately 200-times the 20 mcg/day clinical dose based on mcg/m^2.

Insulin glargine

Subcutaneous reproduction and teratology studies have been performed with insulin glargine and regular human insulin in rats and Himalayan rabbits. Insulin glargine was given to female rats before mating, during mating, and throughout pregnancy at doses up to 0.36 mg/kg/day, which is approximately 2-times the recommended human subcutaneous high dose of 60 units/day (0.0364 mg/kg/day), based on mg/m^2. In rabbits, doses up to 0.072 mg/kg/day, which is approximately 1-time the maximum recommended human subcutaneous dose of 60 units/day (0.0364 mg/kg/day), based on mg/m^2, were administered during organogenesis. The effects of insulin glargine did not generally differ from those observed with regular human insulin in rats or rabbits. However, in rabbits, five fetuses from two litters of the high-dose group exhibited dilation of the cerebral ventricles. Fertility and early embryonic development appeared normal.

8.2 Lactation

Risk Summary

There is no information regarding the presence of lixisenatide and insulin glargine in human milk, the effects on the breastfed infant, or the effects on milk production. Endogenous insulin is present in human milk. Lixisenatide is present in rat milk [see Data].

The developmental and health benefits of breastfeeding should be considered along with the mother's clinical need for SOLIQUA 100/33 and any potential adverse effects on the breastfed child from SOLIQUA 100/33 or from the underlying maternal condition.

Data

Lixisenatide

A study in lactating rats showed low (9.4%) transfer of lixisenatide and its metabolites into milk and negligible (0.01%) levels of unchanged lixisenatide protein in the gastric contents of weaning offspring.

8.4 Pediatric Use

Safety and effectiveness of SOLIQUA 100/33 have not been established in pediatric patients.

8.5 Geriatric Use

Of the total number of subjects (n=834) in controlled clinical studies of patients with type 2 diabetes, who were treated with SOLIQUA 100/33, 25.2% (n=210) were ≥65 years of age and 4% (n=33) were ≥75 years of age. No overall differences in effectiveness and safety were observed in the subgroup analyses across the age groups.

Nevertheless, caution should be exercised when SOLIQUA 100/33 is administered to geriatric patients. In elderly patients with diabetes, the initial dosing, dose increments, and maintenance dosage should be conservative to avoid hypoglycemic reactions. Hypoglycemia may be difficult to recognize in the elderly.

8.6 Renal Impairment

Frequent glucose monitoring and dose adjustment may be necessary for SOLIQUA 100/33 in patients with renal impairment [see Warnings and Precautions (5.7)].

Insulin Glargine

Some studies with human insulin have shown increased circulating levels of insulin in patients with renal failure.

Lixisenatide

In patients with mild and moderate renal impairment no dose adjustment is required but close monitoring for lixisenatide related adverse reactions and for changes in renal function is recommended because of higher incidences of hypoglycemia, nausea and vomiting that were observed in these patients. Increased gastrointestinal adverse reactions may lead to dehydration and acute renal failure and worsening of chronic failure in these patients.

Clinical experience in patients with severe renal impairment is limited as there were only 5 patients with severe renal impairment (eGFR 15 to less than 30 mL/min/1.73 m^2) exposed to lixisenatide in all controlled studies. Lixisenatide exposure was higher in these patients [see Clinical Pharmacology (12.3)]. Patients with severe renal impairment exposed to lixisenatide should be closely monitored for occurrence of gastrointestinal adverse reactions and for changes in renal function.

There is no therapeutic experience in patients with end-stage renal disease (eGFR <15 mL/min/1.73 m^2), and it is not recommended to use SOLIQUA 100/33 in this population.

8.7 Hepatic Impairment

The effect of hepatic impairment on the pharmacokinetics of SOLIQUA 100/33 has not been studied. Frequent glucose monitoring and dose adjustment may be necessary for SOLIQUA 100/33 in patients with hepatic impairment [see Warnings and Precautions (5.6)].

10 OVERDOSAGE

Insulin Glargine

Excess insulin administration may cause hypoglycemia and hypokalemia [see Warnings and Precautions (5.6, 5.10)]. Mild episodes of hypoglycemia can usually be treated with oral carbohydrates. Adjustments in drug dosage, meal patterns, or exercise may be needed.

More severe episodes of hypoglycemia with coma, seizure, or neurologic impairment may be treated with intramuscular/subcutaneous glucagon or concentrated intravenous glucose. After apparent clinical recovery from hypoglycemia, continued observation and additional carbohydrate intake may be necessary to avoid recurrence of hypoglycemia. Hypokalemia must be corrected appropriately.

Lixisenatide

During clinical studies, doses up to 30 mcg of lixisenatide twice daily (3-times the daily recommended dose) were administered to type 2 diabetic patients in a 13-week study. An increased incidence of gastrointestinal disorders was observed.

In case of overdose, consider contacting the Poison Help line (1-800-222-1222) or a medical toxicologist for additional overdosage management recommendations. Initiate appropriate supportive treatment according to the patient's clinical signs and symptoms and the SOLIQUA 100/33 dose should be reduced to the prescribed dose.

11 DESCRIPTION

SOLIQUA 100/33 is a combination of insulin glargine, an insulin analog, and lixisenatide, a GLP-1 receptor agonist.

Insulin glargine is a human insulin analog produced by recombinant DNA technology utilizing a nonpathogenic laboratory strain of Escherichia coli (K12) as the production organism. The minimum potency of insulin glargine is NLT 15 units/mg. Insulin glargine differs from human insulin in that the amino acid asparagine at position A21 is replaced by glycine and two arginines are added at the C-terminus of the B-chain. Insulin glargine has low aqueous solubility at neutral pH. At pH 4 insulin glargine is completely soluble. It has a molecular weight of 6.063 kDa.

Lixisenatide is a synthetic analogue of human GLP-1, which acts as a GLP-1 receptor agonist. Lixisenatide is a protein containing 44 amino acids, which is amidated at the C-terminal amino acid (position 44) and has a molecular weight of 4.8585 kDa.

SOLIQUA 100/33 (insulin glargine and lixisenatide) injection is a sterile, colorless to almost colorless solution for subcutaneous use. SOLIQUA 100/33 is supplied as a prefilled single-patient-use disposable pen contain 300 units of insulin glargine and 100 mcg of lixisenatide in 3 mL of a clear, colorless to almost colorless, sterile, and aqueous solution. Each mL contains 100 units of insulin glargine and 33 mcg of lixisenatide and the inactive ingredients: glycerol (20 mg), metacresol (2.7 mg), methionine (3 mg), zinc (30 mcg), and Water for Injection, USP. Hydrochloric acid and/or sodium hydroxide may be added to adjust the pH. The approximate pH is 4.5.

12 CLINICAL PHARMACOLOGY

12.1 Mechanism of Action

SOLIQUA 100/33

SOLIQUA 100/33 is a combination of insulin glargine, a basal insulin analog, and lixisenatide, a GLP-1 receptor agonist.

Insulin glargine

The primary activity of insulin, including insulin glargine, is regulation of glucose metabolism. Insulin and its analogs lower blood glucose by stimulating peripheral glucose uptake, especially by skeletal muscle and fat, and by inhibiting hepatic glucose production. Insulin inhibits lipolysis and proteolysis and enhances protein synthesis.

Lixisenatide

Lixisenatide is a GLP-1 receptor agonist that increases glucose-dependent insulin release, decreases glucagon secretion, and slows gastric emptying.

12.2 Pharmacodynamics

Insulin Glargine

The combination of insulin glargine and lixisenatide has no impact on the pharmacodynamics of insulin glargine. The impact of the combination of insulin glargine and lixisenatide on the pharmacodynamics of lixisenatide has not been studied in phase 1 studies.

Lixisenatide

In a clinical pharmacology study in adults with type 2 diabetes mellitus, lixisenatide reduced fasting plasma glucose and postprandial blood glucose AUC0–300min compared to placebo (-33.8 mg/dL and -387 mg∙h/dL, respectively) following a standardized test meal. The effect on postprandial blood glucose AUC was most notable with the first meal, and the effect was attenuated with later meals in the day.

Treatment with lixisenatide 20 mcg once daily reduced postprandial glucagon levels (AUC0–300min) compared to placebo by -15.6 h∙pmol/L after a standardized test meal in patients with type 2 diabetes.

Cardiac electrophysiology (QTc)

At a dose 1.5-times the recommended dose, lixisenatide does not prolong the QTc interval to any clinically relevant extent.

12.3 Pharmacokinetics

SOLIQUA 100/33

The insulin glargine/lixisenatide ratio has no relevant impact on the PK of insulin glargine in SOLIQUA 100/33.

Compared to administration of lixisenatide alone, the Cmax is lower whereas the AUC is generally comparable when administered as SOLIQUA 100/33. The insulin glargine/lixisenatide ratio has no impact on the PK of lixisenatide in SOLIQUA 100/33. The observed differences in the PK of lixisenatide when given as SOLIQUA 100/33 or alone are not considered to be clinically relevant.

Absorption

After subcutaneous administration of insulin glargine/lixisenatide combinations, insulin glargine showed no pronounced peak. Exposure to insulin glargine ranged from 86% to 101% compared to administration of insulin glargine alone.

After subcutaneous administration of insulin glargine/lixisenatide combinations, the median tmax of lixisenatide was in the range of 2.5 to 3.0 hours. There was a small decrease in Cmax of lixisenatide of 22%–34% compared with separate simultaneous administration of insulin glargine and lixisenatide, which is not likely to be clinically significant. There are no clinically relevant differences in the rate of absorption when lixisenatide is administered subcutaneously in the abdomen, thigh, or arm.

Distribution

The protein binding of lixisenatide is 55%.

Metabolism and elimination

A metabolism study in humans who received insulin glargine alone indicates that insulin glargine is partly metabolized at the carboxyl terminus of the B chain in the subcutaneous depot to form two active metabolites with in vitro activity similar to that of human insulin, M1 (21A-Gly-insulin) and M2 (21A-Gly-des-30B-Thr-insulin). Unchanged drug and these degradation products are also present in the circulation.

Lixisenatide is presumed to be eliminated through glomerular filtration, and proteolytic degradation.

After multiple dose administration in patients with type 2 diabetes, mean terminal half-life was approximately 3 hours and the mean apparent clearance (CL/F) about 35 L/h.

Special populations

Effects of age, body weight, gender, and race

Insulin glargine: Effect of age, race, and gender on the pharmacokinetics of insulin glargine has not been evaluated. In controlled clinical trials in adults with insulin glargine (100 units/mL), subgroup analyses based on age, race, and gender did not show differences in safety and efficacy.

Lixisenatide: Age, body weight, gender, and race were not observed to meaningfully affect the pharmacokinetics of lixisenatide in population PK analyses.

Renal impairment

Lixisenatide: Compared to healthy subjects (N=4), plasma Cmax of lixisenatide was increased by approximately 60%, 42%, and 83% in subjects with mild (CLcr 60–89 mL/min [N=9]), moderate (CLcr 30–59 mL/min [N=11]), and severe (CLcr 15–29 mL/min [N=8]) renal impairment. Plasma AUC was increased by approximately 34%, 69% and 124% with mild, moderate, and severe renal impairment, respectively [see Use in Specific Populations (8.6)].

Drug interaction studies with SOLIQUA 100/33

Insulin glargine and lixisenatide have no relevant potential to induce or inhibit CYP isozymes and, therefore, no direct drug interaction is expected.

Beyond the interaction studies performed with the individual components no additional interaction studies were conducted with SOLIQUA 100/33.

Drug interaction studies with lixisenatide

The drug interaction studies focused on the potential for lixisenatide to influence the rate and extent of exposure to coadministered drugs due to its known delaying effect on gastric emptying.

Acetaminophen

Lixisenatide 10 mcg did not change the overall exposure (AUC) of acetaminophen following administration of a single dose of acetaminophen 1000 mg, whether before or after lixisenatide. No effects on acetaminophen Cmax and tmax were observed when acetaminophen was administered 1 hour before lixisenatide. When administered 1 or 4 hours after 10 mcg lixisenatide, Cmax of acetaminophen was decreased by 29% and 31%, respectively, and median tmax was delayed by 2.0 and 1.75 hours, respectively.

Oral contraceptives

Administration of a single dose of an oral contraceptive medicinal product (ethinylestradiol 0.03 mg/levonorgestrel 0.15 mg) 1 hour before or 11 hours after 10 mcg lixisenatide, did not change Cmax, AUC, t1/2 and tmax of ethinylestradiol and levonorgestrel.

Administration of the oral contraceptive 1 hour or 4 hours after lixisenatide did not affect the overall exposure (AUC) and mean terminal half-life (t1/2) of ethinylestradiol and levonorgestrel. However, Cmax of ethinylestradiol was decreased by 52% and 39%, respectively, and Cmax of levonorgestrel was decreased by 46% and 20%, respectively, and median tmax was delayed by 1 to 3 hours.

Atorvastatin

When lixisenatide 20 mcg and atorvastatin 40 mg were coadministered in the morning for 6 days, the exposure of atorvastatin was not affected, while Cmax was decreased by 31% and tmax was delayed by 3.25 hours. No such increase for tmax was observed when atorvastatin was administered in the evening and lixisenatide in the morning but the AUC and Cmax of atorvastatin were increased by 27% and 66%, respectively.

Warfarin and other coumarin derivatives

After concomitant administration of warfarin 25 mg with repeated dosing of lixisenatide 20 mcg, there were no effects on AUC or INR (International Normalized Ratio) while Cmax was reduced by 19% and tmax was delayed by 7 hours.

Digoxin

After concomitant administration of lixisenatide 20 mcg and digoxin 0.25 mg at steady state, the AUC of digoxin was not affected. The tmax of digoxin was delayed by 1.5 hour and the Cmax was reduced by 26%.

Ramipril

After concomitant administration of lixisenatide 20 mcg and ramipril 5 mg for 6 days, the AUC of ramipril was increased by 21% while the Cmax was decreased by 63%. The AUC and Cmax of the active metabolite (ramiprilat) were not affected. The tmax of ramipril and ramiprilat were delayed by approximately 2.5 hours.

13 NONCLINICAL TOXICOLOGY

13.1 Carcinogenesis, Mutagenesis, Impairment of Fertility

SOLIQUA 100/33

No animal studies have been conducted with the combination of insulin glargine and lixisenatide to evaluate carcinogenesis, mutagenesis, or impairment of fertility.

Insulin glargine

In mice and rats, standard two-year carcinogenicity studies with insulin glargine were performed at doses up to 0.455 mg/kg, which was for the rat approximately 2-times and for the mouse approximately 1-times the recommended human subcutaneous high dose of 60 units/day (0.0364 mg/kg/day), based on mg/m^2. The findings in female mice were not conclusive due to excessive mortality in all dose groups during the study. Histiocytomas were found at injection sites in male rats (statistically significant) and male mice (not statistically significant) in acid vehicle containing groups. These tumors were not found in female animals, in saline control, or insulin comparator groups using a different vehicle. The relevance of these findings to humans is unknown.

Insulin glargine was not mutagenic in tests for detection of gene mutations in bacteria and mammalian cells (Ames- and HGPRT-test) and in tests for detection of chromosomal aberrations (cytogenetics in vitro in V79 cells and in vivo in Chinese hamsters).

In a combined fertility and prenatal and postnatal study with insulin glargine in male and female rats at subcutaneous doses up to 0.36 mg/kg/day, which was approximately 2-times the recommended human subcutaneous maximum dose of 60 units/day (0.0364 mg/kg/day), based on mg/m^2, maternal toxicity due to dose-dependent hypoglycemia, including some deaths, was observed. Consequently, a reduction of the rearing rate occurred in the high-dose group only.

Lixisenatide

Carcinogenicity studies of 2-years durations were conducted in CD-1 mice and Sprague-Dawley rats with twice daily subcutaneous doses of 40, 200, or 1000 mcg/kg. A statistically significant increase in thyroid C-cell adenomas was observed in males at 2,000 mcg/kg/day, resulting in exposures that are >180-times the human exposure achieved at 20 mcg/day based on plasma AUC.

Statistically significant increases in thyroid C-cell adenomas were seen at all doses in rats, resulting in systemic exposures that are ≥15-times the human exposure achieved at 20 mcg/day based on plasma AUC. A numerical increase in thyroid C-cell carcinomas was observed in rats at ≥400 mcg/kg/day, resulting in systemic exposures that are ≥56-times the human exposure achieved at 20 mcg/day based on plasma AUC.

Mutagenesis

Lixisenatide was not mutagenic or clastogenic in a standard battery of genotoxicity tests (bacterial mutagenicity [Ames], human lymphocyte chromosome aberration, mouse bone marrow micronucleus).

Impairment of fertility

Studies in which male and female rats received twice daily subcutaneous doses lixisenatide of 2, 29, or 414 mcg/kg prior to pairing through gestation day 6 did not indicate any adverse effects on male or female fertility in rats up to the highest dose tested, 414 mcg/kg, or approximately 400-times the clinical systemic exposure at 20 mcg/day based on mcg/m^2.

14 CLINICAL STUDIES

14.1 Overview of Clinical Studies

SOLIQUA 100/33 was evaluated in two randomized clinical studies in patients with type 2 diabetes mellitus. In each of the active-controlled trials, treatment with SOLIQUA 100/33 produced statistically significant improvements in HbA1c.

14.2 Clinical Study in Patients with Type 2 Diabetes Uncontrolled on OAD Treatment

A total of 1170 patients with type 2 diabetes were randomized in an open-label, 30-week, active-controlled study (Study A: NCT05058147) to evaluate the efficacy and safety of SOLIQUA 100/33 compared to the individual components, insulin glargine 100 units/mL and lixisenatide.

Patients with type 2 diabetes, treated with metformin alone or treated with metformin and a second OAD treatment that could be a sulfonylurea or a glinide or a sodium-glucose cotransporter-2 (SGLT-2) inhibitor or a dipeptidyl peptidase-4 (DPP-4) inhibitor, and who were not adequately controlled with this treatment (HbA1c range 7.5% to 10% for patients previously treated with metformin alone and 7% to 9% for patients previously treated with metformin and a second OAD treatment) entered a run-in period for 4 weeks. During this run-in period, metformin treatment was optimized and all other OADs were discontinued. At the end of the run-in period, patients who remained inadequately controlled (HbA1c between 7% and 10%) were randomized to either SOLIQUA 100/33 (n=469), insulin glargine 100 units/mL (n=467), or lixisenatide (n=234).

The type 2 diabetes population had the following characteristics: mean age was 58.4 years, 50.6% were male, 90.1% were Caucasian, 6.7% were Black or African American, and 19.1% were Hispanic. At screening, the mean duration of diabetes was approximately 9 years, the mean BMI was approximately 31.7 kg/m^2, and mean eGFR was 84.8 mL/min/1.73 m^2.

SOLIQUA 100/33 and insulin glargine were to be titrated weekly to target a fasting plasma glucose goal of <100 mg/dL. Patients could not increase their dose by more than 4 units per week and the prespecified maximum dose of insulin glargine was limited to 60 units. The targeted fasting plasma glucose goal was achieved in 35% of patients in both groups at 30 weeks.

At Week 30, SOLIQUA 100/33 provided statistically significant improvement in HbA1c (p-value <0.0001) compared to insulin glargine 100 units/mL and lixisenatide-treated patients (-1.6%, -1.3%, and -0.9%). In a prespecified analysis of this primary endpoint, the differences observed were consistent with regard to baseline OAD use (metformin alone or metformin plus second OAD).

The mean difference (95% CI) in HbA1c reduction between SOLIQUA 100/33 and insulin glargine was -0.3% (-0.4, -0.2) and -0.7% (-0.8, -0.6) compared to lixisenatide.

See Table 5 for the other endpoints in the study. The difference in the glucose lowering effect observed in the trial may not necessarily reflect the effect that will be observed in the care setting where insulin glargine dosage can be different than that used in the trial.

Table 5: Results at 30 Weeks – Add-On to Metformin Clinical Study
 | SOLIQUA 100/33 | Insulin Glargine 100 units/mL | Lixisenatide
Number of subjects (randomized and treated) | 469 | 467 | 233
HbA1c (%)
Baseline (mean; post run-in phase) | 8.1 | 8.1 | 8.1
End of study (mean) | 6.5 | 6.8 | 7.3
LS change from baseline (mean) [Estimated using an ANCOVA with treatment, randomization strata, and country as fixed factors and baseline HbA1c as covariate. Twenty-six (5.5%) patients in the SOLIQUA 100/33 arm and 21 (4.5%) patients in the insulin glargine 100 units/mL arm, and 13 (5.6%) patients in the lixisenatide arm had missing HbA1c measurement at Week 30. Missing measurements were imputed using multiple imputations with respect to the baseline value of the subject.] | -1.6 | -1.3 | -0.9
LS mean difference vs insulin glargine | -0.3
[95% confidence interval] | [-0.4, -0.2] [The trial was designed to show the contribution of the GLP-1 component to glycemic lowering, and the insulin glargine dose and the dosing algorithm were selected to isolate the effect of the GLP-1 component. At the end of the trial, the doses of insulin glargine were equivalent between treatment groups. The mean final dose of SOLIQUA 100/33 at week 30 was 39.8 units (for SOLIQUA 100/33: 39.8 units insulin glargine/13.1 mcg lixisenatide) and 40.5 units in the insulin glargine–treated patients. The difference in effect observed in the trial may not necessarily reflect the effect that will be observed in the care setting where alternative insulin glargine dosage can be used.] |  | –
(p-value) | (<0.0001)
LS mean difference vs lixisenatide |  |  | -0.7
[95% confidence interval] | – | – | [-0.8, -0.6] [Lixisenatide was given at the maintenance dose of 20 mcg.]
(p-value) |  |  | (<0.0001)
Number of Patients (%) reaching HbA1c <7% at week 30 | 345 (74%) | 277 (59%) | 76 (33%)
Fasting plasma glucose (mg/dL)
Baseline (mean) | 177.9 | 175.7 | 175.8
End of study (mean) | 113.9 | 117.6 | 149.0
LS change from baseline (mean) | -59.1 | -55.8 | -27.2

Figure 1: Mean HbA1c (%) Over Time – Randomized and Treated Population

S = Screening (Week 6), R = Run-in (Week 1), B = Baseline, MI = Multiple imputation.
INS/LIXI = fixed ratio combination, INS = Insulin Glargine, LIXI = Lixisenatide
Note: The plot included all scheduled measurements obtained during the study, including those obtained after IMP discontinuation or introduction of rescue medication.
30MI: Missing HbA1c values at Week 30 in each group were imputed using their baseline HbA1c values plus an error. The error is normally distributed with mean zero and a standard deviation set equal to the estimated pooled standard deviation.

14.3 Clinical Studies in Patients with Type 2 Diabetes Uncontrolled on Basal Insulin

A total of 736 patients with type 2 diabetes participated in a randomized, 30-week, active-controlled, open-label, 2-treatment arm, parallel-group, multicenter study (Study B: NCT02058160) to evaluate the efficacy and safety of SOLIQUA 100/33 compared to insulin glargine 100 units/mL.

Patients screened had type 2 diabetes were treated with basal insulin for at least 6 months, receiving a stable daily dose of between 15 and 40 units alone or combined with 1 or 2 OADs (metformin, sulfonylurea, glinide, SGLT-2 inhibitor or a DPP-4 inhibitor), had an HbA1c between 7.5% and 10% and a FPG less than or equal to 180 mg/dL or 200 mg/dL depending on their previous antidiabetic treatment.

This type 2 diabetes population had the following characteristics: Mean age was 60 years, 46.7% were male, 91.7% were Caucasian, 5.2% were Black or African American and 17.9% were Hispanic. At screening, the mean duration of diabetes was approximately 12 years, the mean BMI was approximately 31 kg/m^2, mean eGFR was 80.6 mL/min/1.73 m^2 and 86.1% of patients had an eGFR ≥60 mL/min.

After screening, eligible patients (n=1018) entered a 6-week run-in phase where patients remained on or were switched to insulin glargine 100 units/mL, if they were treated with another basal insulin, and had their insulin glargine dose titrated/stabilized while continuing metformin (if previously taken). The mean HbA1c decreased during run-in period from 8.5% to 8.1%. Any other OADs were discontinued.

At the end of the run-in period, patients with an HbA1c between 7% and 10%, FPG ≤140 mg/dL and insulin glargine daily dose of 20 to 50 units (mean of 35 units), were randomized to either SOLIQUA 100/33 (n=367) or insulin glargine 100 units/mL (n=369).

SOLIQUA 100/33 and insulin glargine were to be titrated weekly to target a fasting plasma glucose goal of <100 mg/dL. The mean dose of insulin glargine at baseline was 35 units. The maximum dose of insulin glargine allowed in the trial was 60 units (insulin dose cap) in both groups. The targeted fasting plasma glucose goal was achieved in 33% of patients in both groups at 30 weeks.

At Week 30, there was a reduction in HbA1c from baseline of -1.1% for SOLIQUA 100/33 and -0.6% for insulin glargine 100 units/mL. The mean difference (95% CI) in HbA1c reduction between SOLIQUA 100/33 and insulin glargine was -0.5 [-0.6, -0.4] and statistically significant. The trial was designed to show the contribution of the GLP-1 component to glycemic lowering and the insulin glargine dose and the dosing algorithm was selected to isolate the effect of the GLP-1 component. At the end of the trial, the doses of insulin glargine were equivalent between treatment groups. The mean final dose of SOLIQUA 100/33 and insulin glargine at week 30 was 46.7 units (for SOLIQUA 100/33: 46.7 units insulin glargine/15.6 mcg lixisenatide). The difference in effect observed in the trial may not necessarily reflect the effect that will be observed in the care setting where alternative insulin glargine dosage can be used. See Table 6 for the other endpoints in the study.

Table 6: Results of a 30-Week Study in Patients with Type 2 Diabetes Mellitus Inadequately Controlled on Basal Insulin
 | SOLIQUA 100/33 | Insulin Glargine 100 units/mL
Number of Subjects (randomized and treated) | 365 | 365
HbA1c (%)
Baseline (mean; post run-in phase) | 8.1 | 8.1
End of study (mean) | 6.9 | 7.5
LS change from baseline (mean) [Estimated using an ANCOVA with treatment, randomization strata, and country as fixed factors and baseline HbA1c as covariate. Twenty (5.5%) patients in the SOLIQUA 100/33 arm and 10 (2.7%) patients in the insulin glargine 100 units/mL arm had missing HbA1c measurement at Week 30. Missing measurements were imputed using multiple imputations with respect to the baseline value of the subject.] | -1.1 | -0.6
Difference vs insulin glargine | -0.5
[95% confidence interval] | [-0.6, -0.4] [p<0.01; The trial was designed to show the contribution of the GLP-1 component to glucose lowering. The insulin glargine dose in this trial was capped at a maximum dose of 60 units and the dosing algorithm was selected to isolate the effect of the GLP-1 component. At the end of the trial, the doses of insulin glargine were equivalent between treatment groups. The mean final dose of SOLIQUA 100/33 and insulin glargine at week 30 was 46.7 units (for SOLIQUA 100/33: 46.7 units insulin glargine/15.6 mcg lixisenatide). The difference in effect observed in the trial may not necessarily reflect the effect that will be observed in the care setting where alternative insulin glargine dosage can be used.]
Patients [n (%)] reaching HbA1c <7% at week 30 [Patients with missing HbA1c measurement at Week 30 were considered non-responders.] | 201 (55.1%) | 108 (29.6%)
Fasting plasma glucose (mg/dL)
Baseline (mean) | 132.3 | 132.0
End of study (mean) | 121.9 | 120.5
LS change from baseline (mean) | -5.7 | -7.0

16 HOW SUPPLIED/STORAGE AND HANDLING

16.1 How Supplied

SOLIQUA 100/33 (insulin glargine and lixisenatide) injection is a clear, colorless to almost colorless solution in a 3 mL prefilled, disposable, single-patient-use pen:

Dosage Unit/Strength | Package size | NDC #
3 mL SOLIQUA 100/33 single-patient-use pen 100 units/mL insulin glargine and 33 mcg/mL lixisenatide | Package of 5 | 0024-5761-05

Needles are not included. Only use needles that are compatible for use with SOLIQUA 100/33 prefilled pen.

16.2 Storage

Dispense in the original sealed carton with the enclosed Instructions for Use.

Prior to first use, SOLIQUA 100/33 pen should be stored in a refrigerator, 36°F–46°F (2°C–8°C). Do not freeze. Discard SOLIQUA 100/33 if it has been frozen. Protect from light.

After first use, store at room temperature up to 77°F (25°C). Replace the pen cap after each use to protect from light.

Discard pen 28 days after first use.

Remove the needle after each injection and store the SOLIQUA 100/33 pen without a needle attached.

17 PATIENT COUNSELING INFORMATION

Advise the patient to read the FDA-approved patient labeling (Medication Guide and Instructions for Use).

Anaphylaxis and Serious Hypersensitivity Reactions

Inform patients that serious hypersensitivity reactions, including anaphylaxis, have been reported with SOLIQUA 100/33. If symptoms of hypersensitivity reactions occur, instruct patients to stop taking SOLIQUA 100/33 and seek medical advice promptly [see Warnings and Precautions (5.1)].

Acute Pancreatitis

Inform patients of the potential risk for acute pancreatitis and its symptoms: severe abdominal pain that may radiate to the back, and which may or may not be accompanied by vomiting. Instruct patients to discontinue SOLIQUA 100/33 promptly and contact their physician if pancreatitis is suspected [see Warnings and Precautions (5.2)].

Never Share SOLIQUA 100/33 Prefilled Pen Between Patients

Advise patients that they must never share a SOLIQUA 100/33 prefilled pen with another person, even if the needle is changed because doing so carries a risk for transmission of blood-borne pathogens [see Warnings and Precautions (5.3)].

Hyperglycemia or Hypoglycemia with Changes in Insulin Regimen

Inform patients that hypoglycemia is the most common adverse reaction with insulin-containing products. Inform patients of the symptoms of hypoglycemia. Inform patients that the ability to concentrate and react may be impaired as a result of hypoglycemia [see Warnings and Precautions (5.6)]. This may present a risk in situations where these abilities are especially important, such as driving or operating other machinery. Advise patients who have frequent hypoglycemia or reduced or absent warning signs of hypoglycemia to use caution when driving or operating machinery.

Advise patients that changes in insulin regimen can predispose to hyperglycemia or hypoglycemia and that changes in insulin regimen should be made under close medical supervision [see Warnings and Precautions (5.4)].

Overdose due to Medication Errors

Inform patients that SOLIQUA 100/33 contains two drugs: insulin glargine and lixisenatide. Accidental mix-ups between insulin products have been reported. To avoid medication errors between SOLIQUA 100/33 and other insulin products, instruct patients to always check the label before each injection. Advise patients that the administration of more than 60 units of SOLIQUA 100/33 daily can result in overdose of the lixisenatide component. Instruct patients not to administer concurrently with other GLP-1 receptor agonists [see Warnings and Precautions (5.5)].

Acute Kidney Injury Due to Volume Depletion

Inform patients of the potential risk of acute kidney injury due to dehydration associated with gastrointestinal adverse reactions. Advise patients to take precautions to avoid fluid depletion. Inform patients of the signs and symptoms of acute kidney injury and instruct them to promptly report any of these signs or symptoms or persistent (or extended) nausea, vomiting, and diarrhea to their healthcare provider [see Warnings and Precautions (5.7)].

Severe Gastrointestinal Adverse Reactions

Inform patients of the potential risk of severe gastrointestinal adverse reactions. Instruct patients to contact their healthcare provider if they have severe or persistent gastrointestinal symptoms [see Warnings and Precautions (5.8)].

Acute Gallbladder Disease

Inform patients of the potential risk for cholelithiasis or cholecystitis. Instruct patients to contact their physician if cholelithiasis or cholecystitis is suspected for appropriate clinical follow-up [see Warnings and Precautions (5.12)].

Pulmonary Aspiration During General Anesthesia or Deep Sedation

Inform patients that SOLIQUA 100/33 may cause their stomach to empty more slowly which may lead to complications with anesthesia or deep sedation during planned surgeries or procedures. Instruct patients to inform healthcare providers prior to any planned surgeries or procedures if they are taking SOLIQUA 100/33 [see Warnings and Precautions (5.13)].

Use in Pregnancy

Advise patients to inform their physicians if they are pregnant or intend to become pregnant [see Use in Specific Populations (8.1)].

Manufactured by:
sanofi-aventis U.S. LLC
Morristown, NJ 07960
A SANOFI COMPANY
U.S. License No. 1752
For patent information: https://www.sanofi.us/en/products-and-resources/patents

©2025 sanofi-aventis U.S. LLC

SOLIQUA and SoloStar are registered trademarks of sanofi-aventis U.S. LLC.

Medication Guide
SOLIQUA® 100/33 (So - lee - kwa)
(insulin glargine and lixisenatide)
injection, for subcutaneous use

What is the most important information I should know about SOLIQUA 100/33?
SOLIQUA 100/33 can cause serious side effects including inflammation of the pancreas (pancreatitis).
Stop using SOLIQUA 100/33 and call your healthcare provider right away if you have severe pain in your stomach area (abdomen) that will not go away, with or without vomiting. You may feel the pain from your abdomen to your back.

What is SOLIQUA 100/33?
SOLIQUA 100/33 is an injectable prescription medicine that contains 2 diabetes medicines, insulin glargine and lixisenatide, that is used along with diet and exercise to improve blood sugar (glucose) in adults with type 2 diabetes.

- SOLIQUA 100/33 is not recommended for people who also take lixisenatide or other medicines called glucagon-like peptide-1 receptor agonists (GLP-1) receptor agonists.
- SOLIQUA 100/33 is not for use in people with diabetic ketoacidosis.
- SOLIQUA 100/33 has not been studied in people who also take a short-acting (prandial) insulin.
- It is not known if SOLIQUA 100/33 is safe and effective in children.

Who should not use SOLIQUA 100/33?
Do not use SOLIQUA 100/33 if you:

- are having an episode of low blood sugar (hypoglycemia).
- have had a serious allergic reaction to insulin glargine, lixisenatide or any of the other ingredients in SOLIQUA 100/33. See the end of this Medication Guide for a complete list of ingredients in SOLIQUA 100/33. See "What are the possible side effects of SOLIQUA 100/333?" for symptoms of a serious allergic reaction.

Before using SOLIQUA 100/33, tell your healthcare provider about all your medical conditions including if you:

- have or have had problems with your pancreas.
- have heart failure or other heart problems. If you have heart failure, it may get worse while you take thiazolidinediones (TZDs).
- have severe problems with your stomach, such as slowed emptying of your stomach (gastroparesis) or problems with digesting food.
- are taking certain medicines called glucagon-like peptide-1 receptor agonists (GLP-1 receptor agonists).
- are scheduled to have surgery or other procedures that use general anesthesia or deep sleepiness (deep sedation).
- are pregnant or plan to become pregnant. It is not known if SOLIQUA 100/33 will harm your unborn baby. Tell your healthcare provider if you are pregnant or plan to become pregnant while using SOLIQUA 100/33.
- are breastfeeding or plan to breastfeed. It is not known if SOLIQUA 100/33 passes into your breast milk. Talk with your healthcare provider about the best way to feed your baby while you use SOLIQUA 100/33.

Tell your healthcare provider about all the medicines you take, including prescription and over-the-counter medicines, vitamins, and herbal supplements. SOLIQUA 100/33 may affect the way some medicines work and some medicines may affect the way SOLIQUA 100/33 works.
Before using SOLIQUA 100/33, talk to your healthcare provider about low blood sugar and how to manage it.
Especially tell your healthcare provider if you take:

- antibiotics or the pain reliever, acetaminophen. Take these medicines at least 1 hour before using SOLIQUA 100/33. If you must take these medicines, take them with a meal or a snack. You should not take these medicines at the same time that you take SOLIQUA 100/33.
- birth control pills that are taken by mouth (oral contraceptives). SOLIQUA 100/33 may lower the amount of the medicine in your blood from your birth control pills and they may not work as well to prevent pregnancy. Take your birth control pill at least 1 hour before your injection of SOLIQUA 100/33 or at least 11 hours after your SOLIQUA 100/33 injection.

Know the medicines you take. Keep a list of them to show your healthcare provider and pharmacist each time you get a new medicine.

How should I use SOLIQUA 100/33?

- Read the Instructions for Use that comes with SOLIQUA 100/33..
- Use SOLIQUA 100/33 exactly as your healthcare provider tells you to.
- Do not change your dose unless your healthcare provider has told you to change your dose.
- Your healthcare provider should teach you how to inject SOLIQUA 100/33 before you use it for the first time. If you have questions or do not understand the instructions, talk to your healthcare provider.
- Your healthcare provider should show you how to use SOLIQUA 100/33 before you use it for the first time.
- Inject your dose of SOLIQUA 100/33 under the skin (subcutaneously) of your abdomen, thigh or upper arm. Do not use SOLIQUA 100/33 in an insulin pump or inject SOLIQUA 100/33 into your vein (intravenously) or muscle (intramuscularly).
- Use SOLIQUA 100/33 only 1 time each day within 1 hour before the first meal of the day.
- If you miss a dose of SOLIQUA 100/33, take your next scheduled dose at your regular time. Do not take an extra dose or increase your dose to make up for the missed dose.
- Check the label on the SOLIQUA 100/33 pen each time you give your injection to make sure you are using the correct medicine.
- Do not take more than 60 units of SOLIQUA 100/33 each day. SOLIQUA 100/33 contains two medicines: insulin glargine and lixisenatide. If you take too much SOLIQUA 100/33, it can cause severe nausea and vomiting. Do not take SOLIQUA 100/33 with other GLP-1 receptor agonists. If you take too much SOLIQUA 100/33, call your healthcare provider or go to the nearest hospital emergency room right away.
- Only use SOLIQUA 100/33 that is clear and colorless to almost colorless. If you see small particles, return it to your pharmacy for a replacement.
- Change (rotate) your injection site within the area you choose with each dose to reduce your risk of getting pits in skin or thickened skin (lipodystrophy) and skin with lumps (localized cutaneous amyloidosis) at the injection sites.
  - Do not use the exact same spot for each injection.
  - Do not inject where the skin has pits, is thickened, or has lumps.
  - Do not inject where the skin is tender, bruised, scaly or hard, or into scars or damaged skin.
- Do not mix SOLIQUA 100/33 in any other type of insulin or liquid medicine prior to injection.
- Do not remove SOLIQUA 100/33 from the throw away (disposable) prefilled pen with a syringe.
- Do not reuse or share your needles with other people. You may give other people a serious infection, or get a serious infection from them.
- If you take too much SOLIQUA 100/33, call your healthcare provider or the Poison Help line at 1-800-222-1222 or go to the nearest hospital emergency room right away.
- Check your blood sugar levels. Ask your healthcare provider what your blood sugar should be and when you should check your blood sugar levels.

What should I avoid while taking SOLIQUA 100/33?
While taking SOLIQUA 100/33 do not:

- drive or operate heavy machinery, until you know how SOLIQUA 100/33 affects you.
- drink alcohol or use prescription or over-the-counter medicines that contain alcohol.

What are the possible side effects of SOLIQUA 100/33?
SOLIQUA 100/33 can cause serious side effects including:

- See "What is the most important information I should know about SOLIQUA 100/33?"
- severe allergic reactions. Stop taking SOLIQUA 100/33 and get medical help right away if you have any symptoms of a severe allergic reaction including

- swelling of your face, lips, tongue or throat
- problems breathing or swallowing
- severe rash or itching

- fainting or feeling dizzy
- very rapid heartbeat

- low blood sugar (hypoglycemia). Your risk for getting low blood sugar is higher if you take another medicine that can cause low blood sugar.
- Signs and symptoms of low blood sugar may include:

- Dizziness or light-headedness
- sweating
- confusion or drowsiness
- headache

- blurred vision
- slurred speech
- shakiness
- fast heartbeat

- anxiety, irritability, or mood changes
- hunger
- weakness
- feeling jittery

- dehydration leading to kidney problems. Diarrhea, nausea, and vomiting may cause a loss of fluids (dehydration) which may cause kidney problems. It is important for you to drink fluids to help reduce your chance of dehydration. Tell your healthcare provider right away if you have nausea, vomiting, or diarrhea that does not go away.
- Severe stomach problems. Stomach problems, sometimes severe, have been reported in people who use SOLIQUA 100/33. Tell your healthcare provider if you have stomach problems that are severe or will not go away.
- low potassium in your blood (hypokalemia).
- heart failure. Taking certain diabetes pills called TZDs with SOLIQUA 100/33 may cause heart failure in some people. This can happen even if you have never had heart failure or heart problems before. If you already have heart failure it may get worse while you take TZDs with SOLIQUA 100/33. Your healthcare provider should monitor you closely while you are taking TZDs with SOLIQUA 100/33. Tell your healthcare provider if you have any new or worse symptoms of heart failure including shortness of breath, swelling of your ankles or feet, or sudden weight gain. Treatment with TZDs and SOLIQUA 100/33 may need to be adjusted or stopped by your healthcare provider if you have new or worse heart failure.
- gallbladder problems. Gallbladder problems have happened in some people who take SOLIQUA 100/33. Tell your healthcare provider right away if you get symptoms of gallbladder problems which may include:

- pain in your upper stomach (abdomen)
- fever

- yellowing of skin or eyes (jaundice)
- clay-colored stools

- food or liquid getting into the lungs during surgery or other procedures that use general anesthesia or deep sleepiness (deep sedation). SOLIQUA 100/33 may increase the chance of food getting into your lungs during surgery or other procedures. Tell all your healthcare providers that you are taking SOLIQUA 100/33 before you are scheduled to have surgery or other procedures.

The most common side effects of SOLIQUA 100/33 include:

- low blood sugar (hypoglycemia)
- nausea
- stuffy or runny nose and sore throat

- diarrhea
- upper respiratory tract infection
- headache

Talk to your healthcare provider about any side effect that bothers you or does not go away.
These are not all the possible side effects of SOLIQUA 100/33
Call your doctor for medical advice about side effects. You may report side effects to FDA at 1-800-FDA-1088.

How should I store SOLIQUA 100/33?

- Store your new, unused SOLIQUA 100/33 pen in the refrigerator at 36°F to 46°F (2°C to 8°C). Protect the pen from light.
- After first use, store your SOLIQUA 100/33 pen at room temperature no higher than 77°F (25°C).
- Do not freeze SOLIQUA 100/33 pens and do not use SOLIQUA 100/33 if it has been frozen.
- Replace the pen cap after each use to protect from light.
- After first use, use the SOLIQUA 100/33 pen for up to 28 days. Throw away the used SOLIQUA 100/33 pen after 28 days, even if there is some medicine left in the pen.
- Do not use SOLIQUA 100/33 past the expiration date printed on the carton and pen label.
- Do not store the SOLIQUA 100/33 pen with the needle attached. If the needle is left on, this might lead to contamination and cause air bubbles which might affect your dose of medicine.
- See the Instructions for Use about the right way to throw away the SOLIQUA 100/33 pen.
- Keep your SOLIQUA 100/33 pen, pen needles, and all medicines out of the reach of children.

General information about the safe and effective use of SOLIQUA 100/33.
Medicines are sometimes prescribed for purposes other than those listed in a Medication Guide. Do not use SOLIQUA 100/33 for a condition for which it was not prescribed. Do not give SOLIQUA 100/33 to other people, even if they have the same symptoms that you have. It may harm them.
You can ask your pharmacist or healthcare provider for information about SOLIQUA 100/33 that is written for health professionals.

What are the ingredients in SOLIQUA 100/33?
Active ingredients: insulin glargine and lixisenatide
Inactive ingredients: glycerol (20 mg), metacresol (2.7 mg), methionine (3 mg), zinc (30 mcg) and Water for Injection, USP. Hydrochloric acid and/or sodium hydroxide are added as needed to adjust the pH.

Manufactured by: sanofi-aventis U.S. LLC, Morristown, NJ 07960 A SANOFI COMPANY
U.S. License No. 1752
For more information, go to www.soliqua100-33.com or call sanofi-aventis at 1-800-633-1610.

This Medication Guide has been approved by the U.S. Food and Drug Administration.

Revised: July 2025

INSTRUCTIONS FOR USE SOLIQUA® 100/33 (So - lee - kwa) (insulin glargine and lixisenatide) Injection, for subcutaneous use

Read these instructions carefully before using your SOLIQUA 100/33 pen.

Do not share your SOLIQUA 100/33 pen with other people, even if the needle has been changed. You may give other people a serious infection, or get a serious infection from them.

SOLIQUA 100/33 is an injectable prescription medicine that contains 2 diabetes medicines, insulin glargine and lixisenatide in a SoloStar pen. The drug combination in this pen is only for the daily injection of 15 to 60 units of SOLIQUA 100/33. Each unit dialed contains 1 unit insulin glargine and 0.33 mcg lixisenatide.

People who are blind or have other vision problems should not use the SOLIQUA 100/33 pen without help from a person trained to use the pen.

Important information

- Check the label on the SOLIQUA 100/33 pen each time you give your injection to make sure you are using the correct medicine.
- Do not use your pen if it is damaged or if you are not sure that it is working correctly.
- Perform a safety test before each injection (see "Step 3: Do a safety test").
- Always carry a spare pen and spare needles in case they are lost or stop working.
- Do not reuse needles. Always use a new sterile needle for each injection. This helps stop blocked needles, contamination, and infection. If you reuse needles, you might not get your dose (underdosing) or get too much (overdosing).
- Do not use SOLIQUA 100/33 in an insulin pump or inject SOLIQUA 100/33 into your vein (intravenously).
- Do not mix SOLIQUA 100/33 in any other type of insulin or liquid medicine prior to injection.
- Change (rotate) your injection sites within the area you chose with each dose (see "Places to inject").

Learn to inject

- Talk with your healthcare provider about how to use the SOLIQUA 100/33 pen and how to inject correctly before using your pen.
- Ask for help if you have problems handling the pen.
- Read all of these instructions before using your pen. You may get too much or too little medicine if you do not follow the instructions correctly.

Need help?

If you have any questions about your pen or about diabetes, ask your healthcare provider, go to www.soliqua100-33.com or call sanofi-aventis at 1-800-633-1610.

Supplies you will need:

- 1 SOLIQUA 100/33 pen
- 1 new sterile needle (see Step 2 "Attach a new needle")
- 1 alcohol swab
- a puncture-resistant container for used needles and pens (see "Throwing your pen away" at the end of this Instructions for Use)

Places to inject

- Inject your SOLIQUA 100/33 dose exactly as your healthcare provider has shown you.
- Inject your SOLIQUA 100/33 dose under the skin (subcutaneously) of your upper legs (thighs), upper arms, or stomach area (abdomen).
- Change (rotate) your injection sites within the area you choose for each dose to reduce your risk of getting pits in skin or thickened skin (lipodystrophy) and skin with lumps (localized cutaneous amyloidosis) at the injection sites.
- Do not inject where the skin has pits, is thickened, or has lumps.
- Do not inject where the skin is tender, bruised, scaly or hard, or into scars or damaged skin.

Get to know your pen

Step 1: Check your pen

Take a new pen out of the refrigerator at least 1 hour before you inject. Cold medicine is more painful to inject.

1A Check the name and expiration date on the label of your pen.
  - Make sure you have the correct medicine. This pen is colored light green with an orange injection button (see the "Get to know your pen" diagram).
  - Do not use your pen after the expiration date on the pen label.

1B Pull off the pen cap.

1C Check that the medicine is clear and colorless to almost colorless.
  - If you see small particles, return it to your pharmacy for a replacement.

1D Wipe the rubber seal with an alcohol swab.

If you have other injector pens

- Making sure you have the correct medicine is especially important if you have other injector pens.

Step 2: Attach a new needle

- Do not reuse needles. Always use a new sterile needle for each injection. This helps stop blocked needles, contamination and infection.
- Only use needles that are meant to be used with SOLIQUA 100/33. Needles are supplied separately. If you do not know what needles to use, ask your healthcare provider or pharmacist.

2A Take a new needle and peel off the protective seal.

2B Keep the needle straight and screw it onto the pen until fixed. Do not over-tighten.

2C Pull off the outer needle cap. Keep this for later.

2D Pull off the inner needle cap and throw it away.

Handling needles

- Take care when handling needles to prevent needle-stick injury and cross-infection.

Step 3: Do a safety test

Perform a safety test before each injection to:

- Check your pen and the needle to make sure they are working properly.
- Make sure that you get the correct dose.

3A Select 2 units by turning the dose selector until the dose pointer is at the 2 mark.

3B Press the injection button all the way in.
  - When the medicine comes out of the needle tip, your pen is working correctly.

If no liquid appears:

- You may need to repeat this step up to 3 times before seeing the medicine.
- If no medicine comes out after the third time, the needle may be blocked. If this happens:
  - change the needle (see Step 6 to remove the needle and Step 2 to attach a new needle),
  - then repeat the safety test (see Step 3A).
- Do not use your pen if still no medicine comes out of the needle tip. Use a new pen.
- Do not use a syringe to remove medicine from your pen.

If you see air bubbles

- You may see air bubbles in the medicine. This is normal, they will not harm you.

Step 4: Select the dose

- Do not select a dose or press the injection button without a needle attached. This may damage your pen.
- Only use this pen to inject your daily dose from 15 to 60 units. Do not change your dose unless your healthcare provider has told you to change your dose.
- Do not use this pen if you need a single daily dose that is more than 60 units.
- Do not use the pen if your single daily dose is less than 15 units, the black area in dose window as shown in the picture.

4A Make sure a needle is attached and the dose is set to "0".

4B Turn the dose selector until the dose pointer lines up with your dose.
  - Do not dial your dose by counting the clicks, because you might dial the wrong dose. Always check the number in the dose window to make sure you dialed the correct dose.
  - If you turn past your dose, you can turn back down.
  - If there are not enough units left in your pen for your dose, the dose selector will stop at the number of units left.
  - If you cannot select your full prescribed dose, use a new pen.

How to read the dose window

- Each line in the dose window equals 1 unit of SOLIQUA 100/33.
- Even numbers are shown in line with the dose pointer, as shown in picture.

30 units selected

- Odd numbers are shown as a line between even numbers, as shown in picture.

29 units selected

Units of medicine in your pen

- This pen contains 300 units of SOLIQUA 100/33 and it is intended to be used for more than one dose.

Step 5: Inject your dose

If you find it hard to press the injection button in, do not force it as this may break your pen. See the section after Step 5E below for help.

5A Choose a place to inject as shown in the picture labeled "Places to inject."
5B Push the needle into your skin as shown by your healthcare provider.
  - Do not touch the injection button yet.

5C Place your thumb on the injection button. Then press all the way in and hold.
  - Do not press injection button at an angle. Your thumb could block the dose selector from turning.

5D Keep the injection button held in and when you see "0" in the dose window, slowly count to 10.
  - This will make sure you get your full dose.

5E After holding and slowly counting to 10, release the injection button. Then remove the needle from your skin.

If you find it hard to press the injection button in:

- Change the needle (see Step 6 to remove the needle and Step 2 to attach a new needle) then do a safety test (see Step 3).
- If you still find it hard to press in, get a new pen.
- Do not use a syringe to remove medicine from your pen.

Step 6: Remove the needle

- Take care when handling needles to prevent needle-stick injury and cross-infection.
- Do not put the inner needle cap back on.

6A Grip the widest part of the outer needle cap. Keep the needle straight and guide it into the outer needle cap back. Then push firmly on.
  - The needle can puncture the cap if it is recapped at an angle.

6B Grip and squeeze the widest part of the outer needle cap. Turn your pen several times with your other hand to remove the needle.
  - Try again if the needle does not come off the first time.

6C Throw away the used needle in a puncture-resistant container (see "Throwing your pen away" at the end of this Instructions for Use).

6D Put your pen cap back on.
  - Do not put the pen back in the refrigerator.

Use by

- Only use your pen for up to 28 days after its first use.

How to store your pen

Before first use

- Keep new pens in the refrigerator between 36°F to 46°F (2°C to 8°C).
- Do not freeze. If you accidentally freeze your pen, throw it away.

After first use

- Keep your pen at room temperature, up to 77°F (25°C).
- Do not put your pen back in the refrigerator.
- Do not store your pen with the needle attached.
- Store the pen with your pen cap on.

Keep this pen out of the sight and reach of children.

How to care for your pen

Handle your pen with care

- Do not drop your pen or knock it against hard surfaces.
- If you think that your pen may be damaged, do not try to fix it. Use a new one.

Protect your pen from dust and dirt

- You can clean the outside of your pen by wiping it with a damp cloth (water only). Do not soak, wash or lubricate the pen. This may damage it.

Throwing your pen away

- Put the used SOLIQUA 100/33 pen in a FDA-cleared sharps disposal container right away after use. Do not throw away (dispose of) the SOLIQUA 100/33 pen in your household trash.
- If you do not have a FDA-cleared sharps disposal container, you may use a household container that is:
  - made of a heavy-duty plastic,
  - can be closed with a tight-fitting, puncture-resistant lid, without sharps being able to come out,
  - upright and stable during use,
  - leak-resistant, and
  - properly labeled to warn of hazardous waste inside the container.
- When your sharps disposal container is almost full, you will need to follow your community guidelines for the right way to dispose of your sharps disposal container. There may be state or local laws about how you should throw away used needles and syringes. For more information about safe sharps disposal, and for specific information about sharps disposal in the state that you live in, go to the FDA's website at: http://www.fda.gov/safesharpsdisposal.

Manufactured by:
sanofi-aventis U.S. LLC
Morristown, NJ 07960 A SANOFI COMPANY
U.S. License No. 1752

©2025 sanofi-aventis U.S. LLC

SOLIQUA and SoloStar are registered trademarks of sanofi-aventis U.S. LLC.

This Instructions for Use has been approved by the U.S. Food and Drug Administration.

Revised: July 2025

PRINCIPAL DISPLAY PANEL - 3 mL Pen Carton

NDC 0024-5761-05
Rx only

SOLIQUA® 100/33
(insulin glargine and lixisenatide) injection

For Single Patient Use Only
100 units/mL and 33 mcg/mL
With each unit of insulin glargine,
the pen also delivers 0.33 mcg of lixisenatide
Only for Doses from 15 to 60 Units
For subcutaneous injection only
Dispense with the medication guide

Solution for injection in a SoloStar® disposable insulin delivery device
Never remove medication using a syringe
Do not mix with other insulins
Use only if solution is clear and colorless with no particles visible

Five 3 mL prefilled pens (15 mL total) – Dispense in this sealed carton
*Needles not included (see back panel)

SANOFI